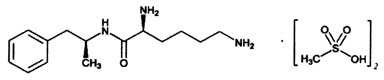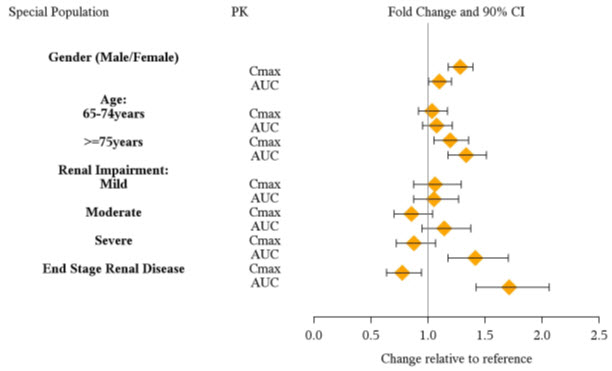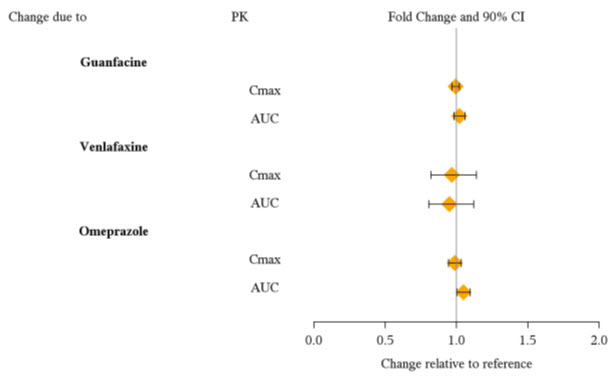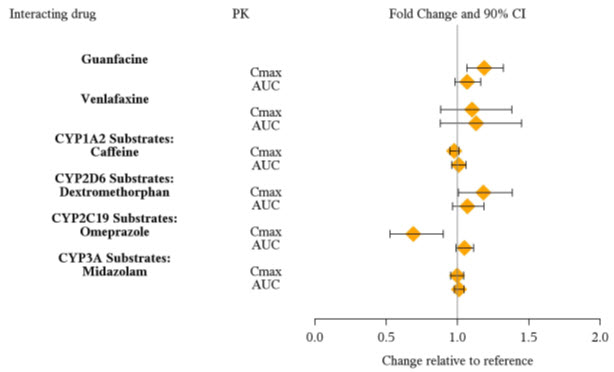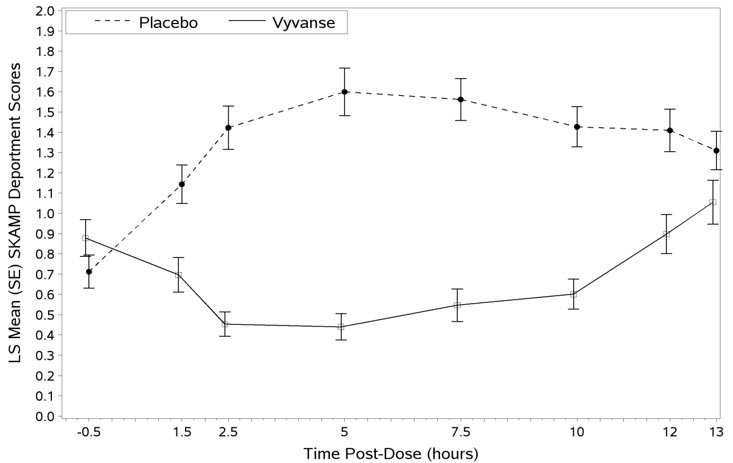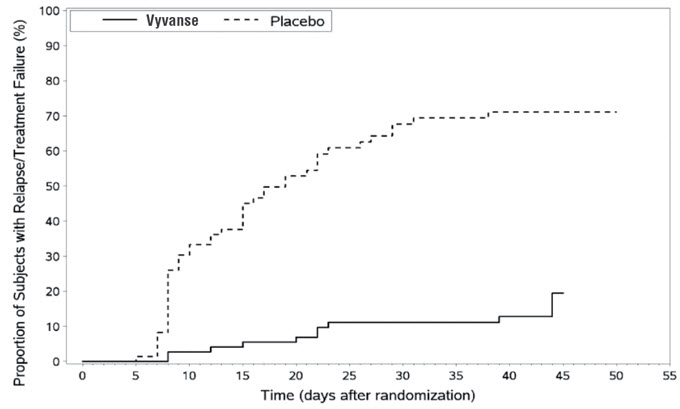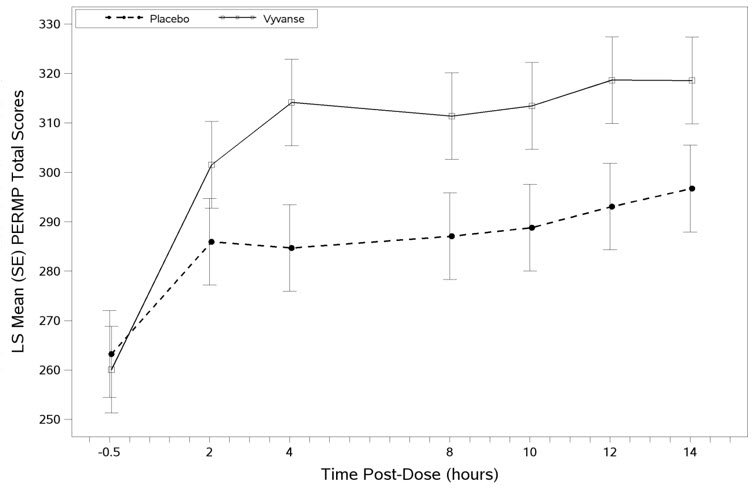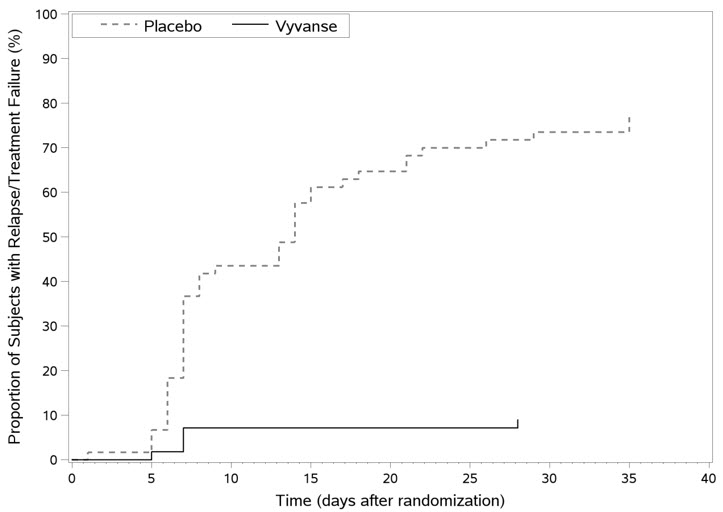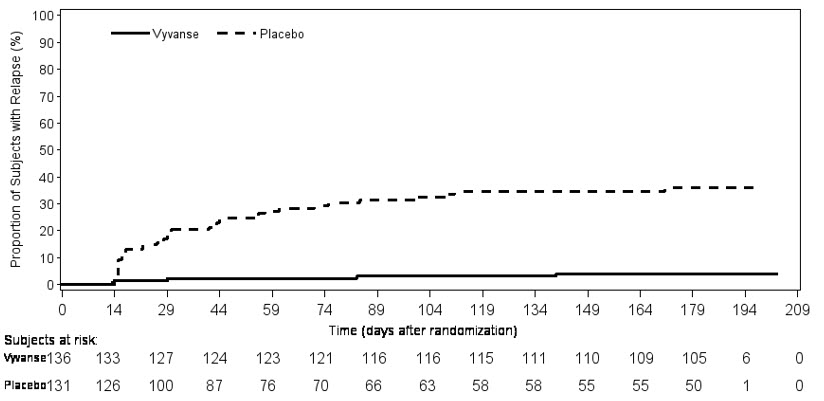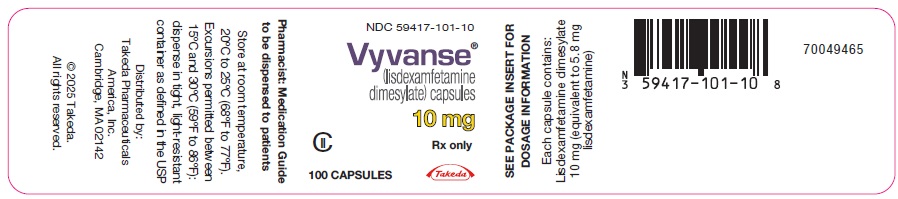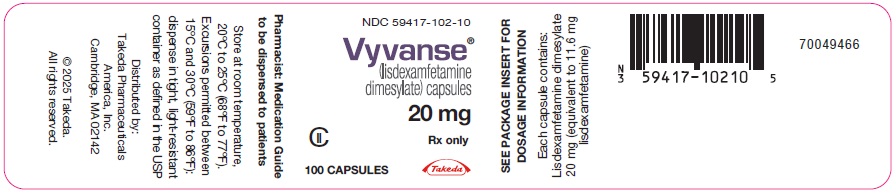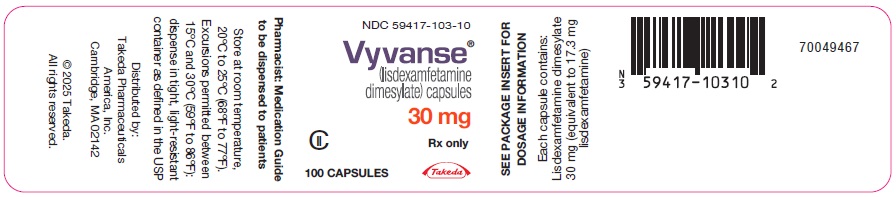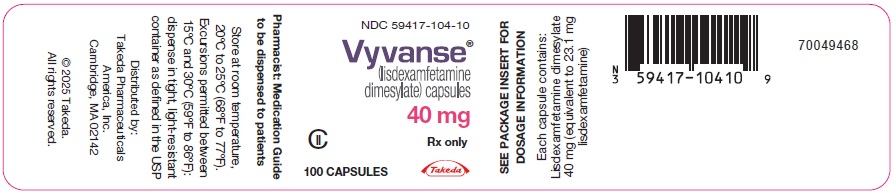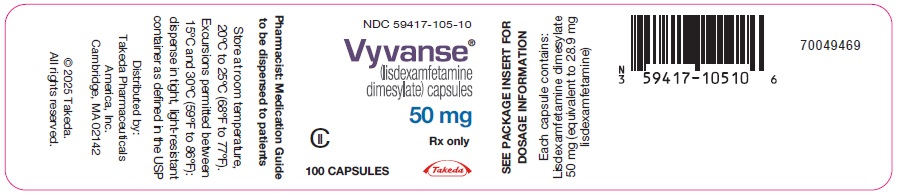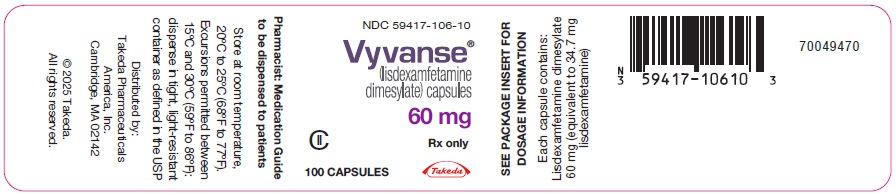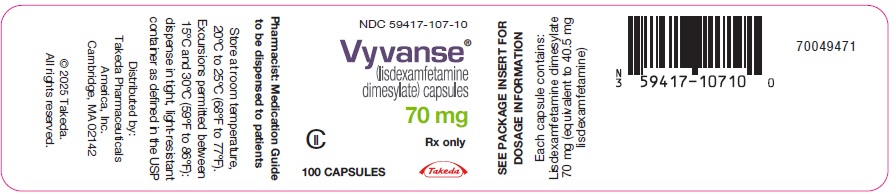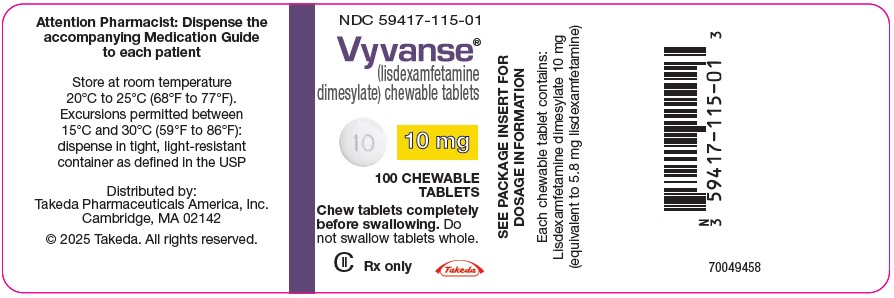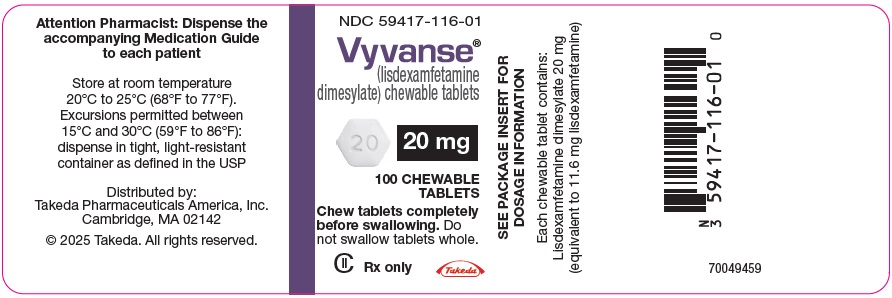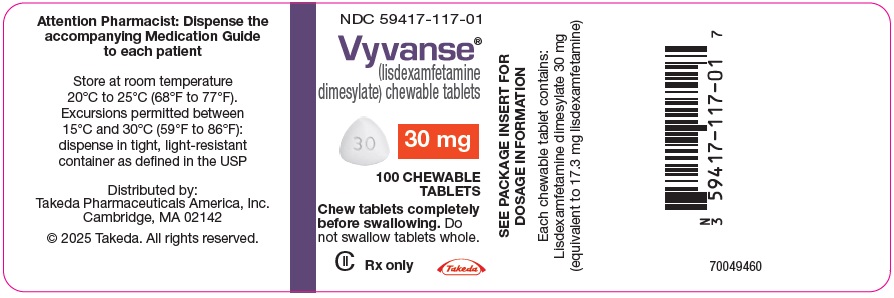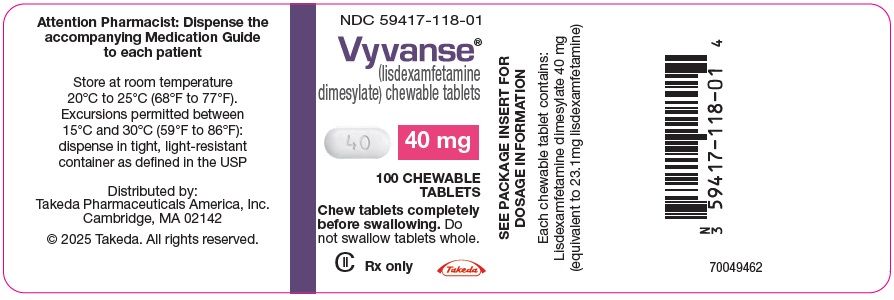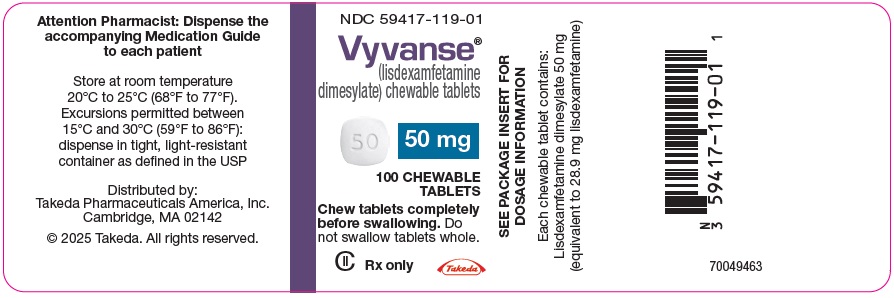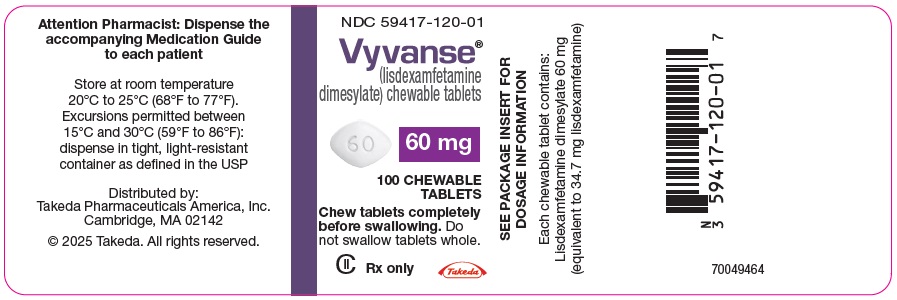 DRUG LABEL: Vyvanse
NDC: 59417-101 | Form: CAPSULE
Manufacturer: Takeda Pharmaceuticals America, Inc.
Category: prescription | Type: HUMAN PRESCRIPTION DRUG LABEL
Date: 20251001
DEA Schedule: CII

ACTIVE INGREDIENTS: LISDEXAMFETAMINE DIMESYLATE 10 mg/1 1
INACTIVE INGREDIENTS: MICROCRYSTALLINE CELLULOSE; CROSCARMELLOSE SODIUM; MAGNESIUM STEARATE; GELATIN, UNSPECIFIED; TITANIUM DIOXIDE; FD&C RED NO. 3

HIGHLIGHTS OF PRESCRIBING INFORMATION

These highlights do not include all the information needed to use VYVANSE safely and effectively. See full prescribing information for VYVANSE.
VYVANSE® (lisdexamfetamine dimesylate) capsules, for oral use, CII
VYVANSE® (lisdexamfetamine dimesylate) chewable tablets, for oral use, CII
Initial U.S. Approval: 2007

WARNING: ABUSE, MISUSE, AND ADDICTION

See full prescribing information for complete boxed warning.

VYVANSE has a high potential for abuse and misuse, which can lead to the development of a substance use disorder, including addiction. Misuse and abuse of CNS stimulants, including VYVANSE, can result in overdose and death (5.1, 9.2, 10):

- Before prescribing VYVANSE, assess each patient's risk for abuse, misuse, and addiction.
- Educate patients and their families about these risks, proper storage of the drug, and proper disposal of any unused drug.
- Throughout treatment, reassess each patient's risk and frequently monitor for signs and symptoms of abuse, misuse, and addiction.

RECENT MAJOR CHANGES

Indications and Usage (1) | 09/2025
Warnings and Precautions (5.5) | 09/2025

1 INDICATIONS AND USAGE

VYVANSE is a central nervous system (CNS) stimulant indicated for the treatment of (1):

- Attention Deficit Hyperactivity Disorder (ADHD) in adults and pediatric patients 6 years and older
- Moderate to severe binge eating disorder (BED) in adults

Limitations of Use:

- The use of VYVANSE is not recommended in pediatric patients younger than 6 years of age because they had higher plasma exposure and a higher incidence of adverse reactions (e.g., weight loss) than patients 6 years and older at the same dosage (5.5, 8.4)
- VYVANSE is not indicated for weight loss. Use of other sympathomimetic drugs for weight loss has been associated with serious cardiovascular adverse events. The safety and effectiveness of VYVANSE for the treatment of obesity have not been established (5.2)

2 DOSAGE AND ADMINISTRATION

Indicated Population | Initial Dose | Titration Schedule | Recommended Dose | Maximum Dose
ADHD (Adults and pediatric patients 6 years and older) (2.2) | 30 mg every morning | 10 mg or 20 mg weekly | 30 mg to 70 mg per day | 70 mg per day
BED (Adults) (2.3) | 30 mg every morning | 20 mg weekly | 50 mg to 70 mg per day | 70 mg per day

- Prior to treatment, assess for presence of cardiac disease (2.4)
- Severe renal impairment: Maximum dose is 50 mg/day (2.5)
- End stage renal disease (ESRD): Maximum dose is 30 mg/day (2.5)

3 DOSAGE FORMS AND STRENGTHS

- Capsules: 10 mg, 20 mg, 30 mg, 40 mg, 50 mg, 60 mg, 70 mg (3)
- Chewable tablets: 10 mg, 20 mg, 30 mg, 40 mg, 50 mg, 60 mg (3)

4 CONTRAINDICATIONS

- Known hypersensitivity to amphetamine products or other ingredients in VYVANSE (4)
- Use with monoamine oxidase (MAO) inhibitor, or within 14 days of the last MAO inhibitor dose (4, 7.1)

5 WARNINGS AND PRECAUTIONS

- Risks to Patients with Serious Cardiac Disease: Avoid use in patients with known structural cardiac abnormalities, cardiomyopathy, serious cardiac arrhythmia, coronary artery disease, or other serious cardiac disease (5.2)
- Increased Blood Pressure and Heart Rate: Monitor blood pressure and pulse. (5.3)
- Psychiatric Adverse Reactions: Prior to initiating VYVANSE, screen patients for risk factors for developing a manic episode. If new psychotic or manic symptoms occur, consider discontinuing VYVANSE. (5.4)
- Long-Term Suppression of Growth in Pediatric Patients: Closely monitor growth (height and weight) in pediatric patients. Pediatric patients not growing or gaining height or weight as expected may need to have their treatment interrupted. (5.5)
- Peripheral Vasculopathy, including Raynaud's phenomenon: Careful observation for digital changes is necessary during VYVANSE treatment. Further clinical evaluation (e.g., rheumatology referral) may be appropriate for patients who develop signs or symptoms of peripheral vasculopathy. (5.6)
- Serotonin Syndrome: Increased risk when co-administered with serotonergic agents (e.g., SSRIs, SNRIs, triptans), but also during overdosage situations. If it occurs, discontinue VYVANSE and initiate supportive treatment. (4, 5.7, 10)
- Motor and Verbal Tics, and Worsening of Tourette's Syndrome: Before initiating VYVANSE, assess the family history and clinically evaluate patients for tics or Tourette's syndrome. Regularly monitor patients for the emergence or worsening of tics or Tourette's syndrome. Discontinue treatment if clinically appropriate. (5.8)

6 ADVERSE REACTIONS

Most common adverse reactions (incidence ≥5% and at a rate at least twice placebo) in pediatric patients ages 6 to 17 years, and/or adults with ADHD were anorexia, anxiety, decreased appetite, decreased weight, diarrhea, dizziness, dry mouth, irritability, insomnia, nausea, upper abdominal pain, and vomiting. (6.1)

Most common adverse reactions (incidence ≥5% and at a rate at least twice placebo) in adults with BED were dry mouth, insomnia, decreased appetite, increased heart rate, constipation, feeling jittery, and anxiety. (6.1)

To report SUSPECTED ADVERSE REACTIONS, contact Takeda Pharmaceuticals at 1-800-828-2088 or FDA at 1-800-FDA-1088 or www.fda.gov/medwatch.

7 DRUG INTERACTIONS

Acidifying and Alkalinizing Agents: Agents that alter urinary pH can alter blood levels of amphetamine. Acidifying agents decrease amphetamine blood levels, while alkalinizing agents increase amphetamine blood levels. Adjust VYVANSE dosage accordingly. (2.6, 7.1)

8 USE IN SPECIFIC POPULATIONS

- Pregnancy: May cause fetal harm (8.1)
- Lactation: Breastfeeding not recommended (8.2)

FULL PRESCRIBING INFORMATION

WARNING: ABUSE, MISUSE, AND ADDICTION

VYVANSE has a high potential for abuse and misuse, which can lead to the development of a substance use disorder, including addiction. Misuse and abuse of CNS stimulants, including VYVANSE, can result in overdose and death [see Overdosage (10)], and this risk is increased with higher doses or unapproved methods of administration, such as snorting or injection.

Before prescribing VYVANSE, assess each patient's risk for abuse, misuse, and addiction. Educate patients and their families about these risks, proper storage of the drug, and proper disposal of any unused drug. Throughout VYVANSE treatment, reassess each patient's risk of abuse, misuse, and addiction and frequently monitor for signs and symptoms of abuse, misuse, and addiction [see Warnings and Precautions (5.1), Drug Abuse and Dependence (9.2)].

1 INDICATIONS AND USAGE

VYVANSE® is indicated for the treatment of:

- Attention Deficit Hyperactivity Disorder (ADHD) in adults and pediatric patients 6 years and older [see Clinical Studies (14.1)].
- Moderate to severe binge eating disorder (BED) in adults [see Clinical Studies (14.2)].

Limitations of Use:

- The use of VYVANSE is not recommended in pediatric patients younger than 6 years of age because they had higher plasma exposure and a higher incidence of adverse reactions (e.g., weight loss) than patients 6 years and older at the same dosage [see Warnings and Precautions (5.5), Use in Specific Populations (8.4)].
- VYVANSE is not indicated or recommended for weight loss. Use of other sympathomimetic drugs for weight loss has been associated with serious cardiovascular adverse events. The safety and effectiveness of VYVANSE for the treatment of obesity have not been established [see Warnings and Precautions (5.2)].

2 DOSAGE AND ADMINISTRATION

2.1 Pretreatment Screening

Prior to treating patients with VYVANSE, assess:

- for the presence of cardiac disease (i.e., perform a careful history, family history of sudden death or ventricular arrhythmia, and physical exam) [see Warnings and Precautions (5.2)].
- the family history and clinically evaluate patients for motor or verbal tics or Tourette's syndrome before initiating VYVANSE [see Warnings and Precautions (5.8)].

2.2 General Administration Information

Take VYVANSE orally in the morning with or without food; avoid afternoon doses because of the potential for insomnia. VYVANSE may be administered in one of the following ways:

Information for VYVANSE capsules:

- Swallow VYVANSE capsules whole, or
- Open capsules, empty and mix the entire contents with yogurt, water, or orange juice. If the contents of the capsule include any compacted powder, a spoon may be used to break apart the powder. The contents should be mixed until completely dispersed. Consume the entire mixture immediately. It should not be stored. The active ingredient dissolves completely once dispersed; however, a film containing the inactive ingredients may remain in the glass or container once the mixture is consumed.

Information for VYVANSE chewable tablets:

- VYVANSE chewable tablets must be chewed thoroughly before swallowing.

VYVANSE capsules can be substituted with VYVANSE chewable tablets on a unit per unit/mg per mg basis (for example, 30 mg capsules for 30 mg chewable tablet) [see Clinical Pharmacology (12.3)].

Do not take anything less than one capsule or chewable tablet per day. A single dose should not be divided.

2.3 Dosage for Treatment of ADHD

The recommended starting dosage in adults and pediatric patients 6 years and older is 30 mg once daily in the morning. Dosage may be adjusted in increments of 10 mg or 20 mg at approximately weekly intervals up to maximum recommended dosage of 70 mg once daily [see Clinical Studies (14.1)].

2.4 Dosage for Treatment of Moderate to Severe BED in Adults

The recommended starting dosage in adults is 30 mg once daily to be titrated in increments of 20 mg at approximately weekly intervals to achieve the recommended target dose of 50 mg to 70 mg once daily. The maximum recommended dosage is 70 mg once daily [see Clinical Studies (14.2)]. Discontinue VYVANSE if binge eating does not improve.

2.5 Dosage in Patients with Renal Impairment

In patients with severe renal impairment (GFR 15 to <30 mL/min/1.73 m^2), the maximum dosage should not exceed 50 mg once daily. In patients with end stage renal disease (ESRD, GFR <15 mL/min/1.73 m^2), the maximum recommended dosage is 30 mg once daily [see Use in Specific Populations (8.6)].

2.6 Dosage Modifications due to Drug Interactions

Agents that alter urinary pH can impact urinary excretion and alter blood levels of amphetamine. Acidifying agents (e.g., ascorbic acid) decrease blood levels, while alkalinizing agents (e.g., sodium bicarbonate) increase blood levels. Adjust VYVANSE dosage accordingly [see Drug Interactions (7.1)].

3 DOSAGE FORMS AND STRENGTHS

VYVANSE (lisdexamfetamine dimesylate) capsules:

- Capsules 10 mg: pink body/pink cap (imprinted with S489 and 10 mg)
- Capsules 20 mg: ivory body/ivory cap (imprinted with S489 and 20 mg)
- Capsules 30 mg: white body/orange cap (imprinted with S489 and 30 mg)
- Capsules 40 mg: white body/blue green cap (imprinted with S489 and 40 mg)
- Capsules 50 mg: white body/blue cap (imprinted with S489 and 50 mg)
- Capsules 60 mg: aqua blue body/aqua blue cap (imprinted with S489 and 60 mg)
- Capsules 70 mg: blue body/orange cap (imprinted with S489 and 70 mg)

VYVANSE (lisdexamfetamine dimesylate) chewable tablets:

- Chewable tablets 10 mg: White to off-white round shaped tablet debossed with '10' on one side and 'S489' on the other
- Chewable tablets 20 mg: White to off-white hexagonal shaped tablet debossed with '20' on one side and 'S489' on the other
- Chewable tablets 30 mg: White to off-white arc triangular shaped tablet debossed with '30' on one side and 'S489' on the other
- Chewable tablets 40 mg: White to off-white capsule shaped tablet debossed with '40' on one side and 'S489' on the other
- Chewable tablets 50 mg: White to off-white arc square shaped tablet debossed with '50' on one side and 'S489' on the other
- Chewable tablets 60 mg: White to off-white arc diamond shaped tablet debossed with '60' on one side and 'S489' on the other

4 CONTRAINDICATIONS

VYVANSE is contraindicated in patients with:

- Known hypersensitivity to amphetamine products or other ingredients of VYVANSE. Anaphylactic reactions, Stevens-Johnson Syndrome, angioedema, and urticaria have been observed in postmarketing reports [see Adverse Reactions (6.2)].
- Patients taking monoamine oxidase inhibitors (MAOIs), or within 14 days of stopping MAOIs (including MAOIs such as linezolid or intravenous methylene blue), because of an increased risk of hypertensive crisis [see Warnings and Precautions (5.7) and Drug Interactions (7.1)].

5 WARNINGS AND PRECAUTIONS

5.1 Abuse, Misuse, and Addiction

VYVANSE has a high potential for abuse and misuse. The use of VYVANSE exposes individuals to the risks of abuse and misuse, which can lead to the development of a substance use disorder, including addiction. VYVANSE can be diverted for non-medical use into illicit channels or distribution [see Drug Abuse and Dependence (9.2)]. Misuse and abuse of CNS stimulants, including VYVANSE, can result in overdose and death [see Overdosage (10)], and this risk is increased with higher doses or unapproved methods of administration, such as snorting or injection.

Before prescribing VYVANSE, assess each patient's risk for abuse, misuse, and addiction. Educate patients and their families about these risks and proper disposal of any unused drug. Advise patients to store VYVANSE in a safe place, preferably locked, and instruct patients to not give VYVANSE to anyone else. Throughout VYVANSE treatment, reassess each patient's risk of abuse, misuse, and addiction and frequently monitor for signs and symptoms of abuse, misuse, and addiction.

5.2 Risks to Patients with Serious Cardiac Disease

Sudden death has been reported in patients with structural cardiac abnormalities or other serious cardiac disease who were treated with CNS stimulants at the recommended ADHD dosage. Avoid VYVANSE use in patients with known structural cardiac abnormalities, cardiomyopathy, serious cardiac arrhythmia, coronary artery disease, or other serious cardiac disease.

5.3 Increased Blood Pressure and Heart Rate

CNS stimulants cause an increase in blood pressure (mean increase about 2 to 4 mm Hg) and heart rate (mean increase about 3 to 6 bpm). Some patients may have larger increases.

Monitor all VYVANSE-treated patients for potential tachycardia and hypertension.

5.4 Psychiatric Adverse Reactions

Exacerbation of Pre-existing Psychosis

CNS stimulants may exacerbate symptoms of behavior disturbance and thought disorder in patients with a pre-existing psychotic disorder.

Induction of a Manic Episode in Patients with Bipolar Disorder

CNS stimulants may induce a manic or mixed episode. Prior to initiating VYVANSE treatment, screen patients for risk factors for developing a manic episode (e.g., comorbid or history of depressive symptoms or a family history of suicide, bipolar disorder, and depression).

New Psychotic or Manic Symptoms

CNS stimulants, at the recommended dosage, may cause psychotic or manic symptoms (e.g., hallucinations, delusional thinking, or mania) in patients without a prior history of psychotic illness or mania. In a pooled analysis of multiple short-term, placebo-controlled studies of CNS stimulants, psychotic or manic symptoms occurred in approximately 0.1% of CNS stimulant-treated patients compared to 0% of placebo-treated patients. If such symptoms occur, consider discontinuing VYVANSE.

5.5 Long-Term Suppression of Growth in Pediatric Patients

VYVANSE is not approved for use and is not recommended in pediatric patients below 6 years of age [see Use in Specific Populations (8.4)].

CNS stimulants have been associated with weight loss and slowing of growth rate in pediatric patients.

In a 4-week, placebo-controlled trial of VYVANSE in pediatric patients ages 6 to 12 years old with ADHD, there was a dose-related decrease in weight in the VYVANSE groups compared to weight gain in the placebo group. Additionally, in studies of another stimulant, there was slowing of the increase in height [see Adverse Reactions (6.1)].

Closely monitor growth (weight and height) in VYVANSE-treated pediatric patients. Patients who are not growing or gaining height or weight as expected may need to have their treatment interrupted.

5.6 Peripheral Vasculopathy, including Raynaud's Phenomenon

CNS stimulants, including VYVANSE, used to treat ADHD are associated with peripheral vasculopathy, including Raynaud's phenomenon. Signs and symptoms are usually intermittent and mild; however, sequelae have included digital ulceration and/or soft tissue breakdown. Effects of peripheral vasculopathy, including Raynaud's phenomenon, were observed in post-marketing reports and at the therapeutic dosages of CNS stimulants in all age groups throughout the course of treatment. Signs and symptoms generally improved after dosage reduction or discontinuation of the CNS stimulant.

Careful observation for digital changes is necessary during VYVANSE treatment. Further clinical evaluation (e.g., rheumatology referral) may be appropriate for VYVANSE-treated patients who develop signs or symptoms of peripheral vasculopathy.

5.7 Serotonin Syndrome

Serotonin syndrome, a potentially life-threatening reaction, may occur when amphetamines are used in combination with other drugs that affect the serotonergic neurotransmitter systems such as monoamine oxidase inhibitors (MAOIs), selective serotonin reuptake inhibitors (SSRIs), serotonin norepinephrine reuptake inhibitors (SNRIs), triptans, tricyclic antidepressants, fentanyl, lithium, tramadol, tryptophan, buspirone, and St. John's Wort [see Drug Interactions (7.1)]. The co-administration with cytochrome P450 2D6 (CYP2D6) inhibitors may also increase the risk with increased exposure to the active metabolite of VYVANSE (dextroamphetamine). In these situations, consider an alternative non-serotonergic drug or an alternative drug that does not inhibit CYP2D6 [see Drug Interactions (7.1)].

Serotonin syndrome symptoms may include mental status changes (e.g., agitation, hallucinations, delirium, and coma), autonomic instability (e.g., tachycardia, labile blood pressure, dizziness, diaphoresis, flushing, hyperthermia), neuromuscular symptoms (e.g., tremor, rigidity, myoclonus, hyperreflexia, incoordination), seizures, and/or gastrointestinal symptoms (e.g., nausea, vomiting, diarrhea).

Concomitant use of VYVANSE with MAOI drugs is contraindicated [see Contraindications (4)].

Discontinue treatment with VYVANSE and any concomitant serotonergic agents immediately if symptoms of serotonin syndrome occur, and initiate supportive symptomatic treatment. If concomitant use of VYVANSE with other serotonergic drugs or CYP2D6 inhibitors is clinically warranted, initiate VYVANSE with lower doses, monitor patients for the emergence of serotonin syndrome during drug initiation or titration, and inform patients of the increased risk for serotonin syndrome.

5.8 Motor and Verbal Tics, and Worsening of Tourette's Syndrome

CNS stimulants, including amphetamine, have been associated with the onset or exacerbation of motor and verbal tics. Worsening of Tourette's syndrome has also been reported [see Adverse Reactions (6.2)].

Before initiating VYVANSE, assess the family history and clinically evaluate patients for tics or Tourette's syndrome. Regularly monitor VYVANSE-treated patients for the emergence or worsening of tics or Tourette's syndrome, and discontinue treatment if clinically appropriate.

6 ADVERSE REACTIONS

The following adverse reactions are discussed in greater detail in other sections of the labeling:

- Known hypersensitivity to amphetamine products or other ingredients of VYVANSE [see Contraindications (4)]
- Hypertensive Crisis When Used Concomitantly with Monoamine Oxidase Inhibitors [see Contraindications (4) and Drug Interactions (7.1)]
- Abuse, Misuse, and Addiction [see Boxed Warning, Warnings and Precautions (5.1), and Drug Abuse and Dependence (9.2, 9.3)]
- Risks to Patients with Serious Cardiac Disease [see Warnings and Precautions (5.2)]
- Increased Blood Pressure and Heart Rate [see Warnings and Precautions (5.3)]
- Psychiatric Adverse Reactions [see Warnings and Precautions (5.4)]
- Long-Term Suppression of Growth in Pediatric Patients [see Warnings and Precautions (5.5)]
- Peripheral Vasculopathy, including Raynaud's phenomenon [see Warnings and Precautions (5.6)]
- Serotonin Syndrome [see Warnings and Precautions (5.7)]
- Motor and Verbal Tics, and Worsening of Tourette's Syndrome [see Warnings and Precautions (5.8)]

6.1 Clinical Trials Experience

Because clinical trials are conducted under widely varying conditions, adverse reaction rates observed in the clinical trials of a drug cannot be directly compared to rates in the clinical trials of another drug and may not reflect the rates observed in practice.

Attention Deficit Hyperactivity Disorder

The safety data in this section is based on data from the 4-week controlled parallel-group clinical studies of VYVANSE in pediatric and adult patients with ADHD [see Clinical Studies (14.1)].

Adverse Reactions Associated with Discontinuation of Treatment in ADHD Clinical Trials

In the controlled trial in pediatric patients ages 6 to 12 years (Study 1), 8% (18/218) of VYVANSE-treated patients discontinued due to adverse reactions compared to 0% (0/72) of placebo-treated patients. The most frequently reported adverse reactions (1% or more and twice rate of placebo) were ECG voltage criteria for ventricular hypertrophy, tic, vomiting, psychomotor hyperactivity, insomnia, decreased appetite and rash [2 instances for each adverse reaction, i.e., 2/218 (1%)]. Less frequently reported adverse reactions (less than 1% or less than twice rate of placebo) included abdominal pain upper, dry mouth, weight decreased, dizziness, somnolence, logorrhea, chest pain, anger and hypertension.

In the controlled trial in pediatric patients ages 13 to 17 years (Study 4), 3% (7/233) of VYVANSE-treated patients discontinued due to adverse reactions compared to 1% (1/77) of placebo-treated patients. The most frequently reported adverse reactions (1% or more and twice rate of placebo) were decreased appetite (2/233; 1%) and insomnia (2/233; 1%). Less frequently reported adverse reactions (less than 1% or less than twice rate of placebo) included irritability, dermatillomania, mood swings, and dyspnea.

In the controlled adult trial (Study 7), 6% (21/358) of VYVANSE-treated patients discontinued due to adverse reactions compared to 2% (1/62) of placebo-treated patients. The most frequently reported adverse reactions (1% or more and twice rate of placebo) were insomnia (8/358; 2%), tachycardia (3/358; 1%), irritability (2/358; 1%), hypertension (4/358; 1%), headache (2/358; 1%), anxiety (2/358; 1%), and dyspnea (3/358; 1%). Less frequently reported adverse reactions (less than 1% or less than twice rate of placebo) included palpitations, diarrhea, nausea, decreased appetite, dizziness, agitation, depression, paranoia and restlessness.

Adverse Reactions Occurring at an Incidence of ≥5% or More Among VYVANSE Treated Patients with ADHD in Clinical Trials

The most common adverse reactions (incidence ≥5% and at a rate at least twice placebo) reported in pediatric patients ages 6 to 17 years, and/or adults were anorexia, anxiety, decreased appetite, decreased weight, diarrhea, dizziness, dry mouth, irritability, insomnia, nausea, upper abdominal pain, and vomiting.

Adverse Reactions Occurring at an Incidence of 2% or More Among VYVANSE Treated Patients with ADHD in Clinical Trials

Adverse reactions reported in the controlled trials in pediatric patients ages, 6 to 12 years (Study 1), pediatric patients ages 13 to 17 years (Study 4), and adult patients (Study 7) treated with VYVANSE or placebo are presented in Tables 1, 2 and 3 below.

Table 1 Adverse Reactions Reported by 2% or More of Pediatric Patients Ages 6 to 12 Years with ADHD Taking VYVANSE and Greater than or Equal to Twice the Incidence in Patients Taking Placebo in a 4-Week Clinical Trial (Study 1)
 | VYVANSE (n=218) | Placebo (n=72)
Decreased Appetite | 39% | 4%
Insomnia | 22% | 3%
Abdominal Pain Upper | 12% | 6%
Irritability | 10% | 0%
Vomiting | 9% | 4%
Weight Decreased | 9% | 1%
Nausea | 6% | 3%
Dry Mouth | 5% | 0%
Dizziness | 5% | 0%
Affect lability | 3% | 0%
Rash | 3% | 0%
Pyrexia | 2% | 1%
Somnolence | 2% | 1%
Tic | 2% | 0%
Anorexia | 2% | 0%

Table 2 Adverse Reactions Reported by 2% or More of Pediatric Patients Ages 13 to 17 Years with ADHD Taking VYVANSE and Greater than or Equal to Twice the Incidence in Patients Taking Placebo in a 4-Week Clinical Trial (Study 4)
 | VYVANSE (n=233) | Placebo (n=77)
Decreased Appetite | 34% | 3%
Insomnia | 13% | 4%
Weight Decreased | 9% | 0%
Dry Mouth | 4% | 1%
Palpitations | 2% | 1%
Anorexia | 2% | 0%
Tremor | 2% | 0%

Table 3 Adverse Reactions Reported by 2% or More of Adult Patients with ADHD Taking VYVANSE and Greater than or Equal to Twice the Incidence in Patients Taking Placebo in a 4-Week Clinical Trial (Study 7)
 | VYVANSE (n=358) | Placebo (n=62)
Decreased Appetite | 27% | 2%
Insomnia | 27% | 8%
Dry Mouth | 26% | 3%
Diarrhea | 7% | 0%
Nausea | 7% | 0%
Anxiety | 6% | 0%
Anorexia | 5% | 0%
Feeling Jittery | 4% | 0%
Agitation | 3% | 0%
Increased Blood Pressure | 3% | 0%
Hyperhidrosis | 3% | 0%
Restlessness | 3% | 0%
Decreased Weight | 3% | 0%
Dyspnea | 2% | 0%
Increased Heart Rate | 2% | 0%
Tremor | 2% | 0%
Palpitations | 2% | 0%

In addition, in the adult population erectile dysfunction was observed in 2.6% of males on VYVANSE and 0% on placebo; decreased libido was observed in 1.4% of subjects on VYVANSE and 0% on placebo.

Weight Loss and Slowing Growth Rate in Pediatric Patients with ADHD

In a controlled trial of VYVANSE in pediatric patients ages 6 to 12 years (Study 1), mean weight loss from baseline after 4 weeks of therapy was -0.9, -1.9, and -2.5 pounds, respectively, for patients receiving 30 mg, 50 mg, and 70 mg of VYVANSE, compared to a 1 pound weight gain for patients receiving placebo. Higher doses were associated with greater weight loss with 4 weeks of treatment. Careful follow-up for weight in pediatric patients ages 6 to 12 years who received VYVANSE over 12 months suggests that consistently medicated pediatric patients (i.e., treatment for 7 days per week throughout the year) have a slowing in growth rate, measured by body weight as demonstrated by an age- and sex-normalized mean change from baseline in percentile, of -13.4 over 1 year (average percentiles at baseline and 12 months were 60.9 and 47.2, respectively). In a 4-week controlled trial of VYVANSE in pediatric patients ages 13 to 17 years, mean weight loss from baseline to endpoint was -2.7, -4.3, and -4.8 lbs., respectively, for patients receiving 30 mg, 50 mg, and 70 mg of VYVANSE, compared to a 2.0 pound weight gain for patients receiving placebo.

Careful follow-up of weight and height in pediatric patients ages 7 to 10 years who were randomized to either methylphenidate or non-medication treatment groups over 14 months, as well as in naturalistic subgroups of newly methylphenidate-treated and non-medication treated pediatric patients over 36 months (to the ages of 10 to 13 years), suggests that consistently medicated pediatric patients ages 7 to 13 years (i.e., treatment for 7 days per week throughout the year) have a temporary slowing in growth rate (on average, a total of about 2 cm less growth in height and 2.7 kg less growth in weight over 3 years), without evidence of growth rebound during this period of development. In a controlled trial of amphetamine (d- to l-enantiomer ratio of 3:1) in pediatric patients ages 13 to 17 years, mean weight change from baseline within the initial 4 weeks of therapy was -1.1 pounds and -2.8 pounds, respectively, for patients receiving 10 mg and 20 mg of amphetamine. Higher doses were associated with greater weight loss within the initial 4 weeks of treatment [see Warnings and Precautions (5.5)].

Weight Loss in Adults with ADHD

In the controlled adult trial (Study 7), mean weight loss after 4 weeks of therapy was 2.8 pounds, 3.1 pounds, and 4.3 pounds, for patients receiving final doses of 30 mg, 50 mg, and 70 mg of VYVANSE, respectively, compared to a mean weight gain of 0.5 pounds for patients receiving placebo.

Binge Eating Disorder

The safety data in this section is based on data from two 12-week parallel group, flexible-dose, placebo-controlled studies in adults with BED [see Clinical Studies 14.2]. Patients with cardiovascular risk factors other than obesity and smoking were excluded.

Adverse Reactions Associated with Discontinuation of Treatment in BED Clinical Trials

In controlled trials of patients ages 18 to 55 years, 5.1% (19/373) of VYVANSE-treated patients discontinued due to adverse reactions compared to 2.4% (9/372) of placebo-treated patients. No single adverse reaction led to discontinuation in 1% or more of VYVANSE-treated patients. Less commonly reported adverse reactions (less than 1% or less than twice rate of placebo) included increased heart rate, headache, abdominal pain upper, dyspnea, rash, insomnia, irritability, feeling jittery and anxiety.

Adverse Reactions Occurring at an Incidence of 5% or More and At Least Twice Placebo Among VYVANSE Treated Patients with BED in Clinical Trials

The most common adverse reactions (incidence ≥5% and at a rate at least twice placebo) reported in adults were dry mouth, insomnia, decreased appetite, increased heart rate, constipation, feeling jittery, and anxiety.

Adverse Reactions Occurring at an Incidence of 2% or More and At Least Twice Placebo Among VYVANSE Treated Patients with BED in Clinical Trials

Adverse reactions reported in the pooled controlled trials in adult patients (Study 11 and 12) treated with VYVANSE or placebo are presented in Table 4 below.

Table 4 Adverse Reactions Reported by 2% or More of Adult Patients with BED Taking VYVANSE and Greater than or Equal to Twice the Incidence in Patients Taking Placebo in 12-Week Clinical Trials (Study 11 and 12)
 | VYVANSE (N=373) | Placebo (N=372)
Dry Mouth | 36% | 7%
Insomnia [Includes all preferred terms containing the word "insomnia."] | 20% | 8%
Decreased Appetite | 8% | 2%
Increased Heart Rate [Includes the preferred terms "heart rate increased" and "tachycardia."] | 7% | 1%
Feeling Jittery | 6% | 1%
Constipation | 6% | 1%
Anxiety | 5% | 1%
Diarrhea | 4% | 2%
Decreased Weight | 4% | 0%
Hyperhidrosis | 4% | 0%
Vomiting | 2% | 1%
Gastroenteritis | 2% | 1%
Paresthesia | 2% | 1%
Pruritus | 2% | 1%
Upper Abdominal Pain | 2% | 0%
Energy Increased | 2% | 0%
Urinary Tract Infection | 2% | 0%
Nightmare | 2% | 0%
Restlessness | 2% | 0%
Oropharyngeal Pain | 2% | 0%

6.2 Postmarketing Experience

The following adverse reactions have been identified during post-approval use of VYVANSE. Because these reactions are reported voluntarily from a population of uncertain size, it is not always possible to reliably estimate their frequency or establish a causal relationship to drug exposure. These events are as follows: cardiomyopathy, mydriasis, diplopia, difficulties with visual accommodation, blurred vision, eosinophilic hepatitis, anaphylactic reaction, hypersensitivity, dyskinesia, dysgeusia, motor and verbal tics, bruxism, depression, dermatillomania, alopecia, aggression, Stevens-Johnson Syndrome, chest pain, angioedema, urticaria, seizures, libido changes, frequent or prolonged erections, constipation, rhabdomyolysis, and intestinal ischemia.

7 DRUG INTERACTIONS

7.1 Drugs Having Clinically Important Interactions with Amphetamines

Table 5 Drugs having clinically important interactions with amphetamines.
MAO Inhibitors (MAOI)
Clinical Impact | MAOI antidepressants slow amphetamine metabolism, increasing amphetamines effect on the release of norepinephrine and other monoamines from adrenergic nerve endings causing headaches and other signs of hypertensive crisis. Toxic neurological effects and malignant hyperpyrexia can occur, sometimes with fatal results.
Intervention | Do not administer VYVANSE during or within 14 days following the administration of MAOI [see Contraindications (4)].
Serotonergic Drugs
Clinical Impact | The concomitant use of VYVANSE and serotonergic drugs increases the risk of serotonin syndrome.
Intervention | Initiate with lower doses and monitor patients for signs and symptoms of serotonin syndrome, particularly during VYVANSE initiation or dosage increase. If serotonin syndrome occurs, discontinue VYVANSE and the concomitant serotonergic drug(s) [see Warnings and Precautions (5.7)].
CYP2D6 Inhibitors
Clinical Impact | The concomitant use of VYVANSE and CYP2D6 inhibitors may increase the exposure of dextroamphetamine, the active metabolite of VYVANSE compared to the use of the drug alone and increase the risk of serotonin syndrome.
Intervention | Initiate with lower doses and monitor patients for signs and symptoms of serotonin syndrome particularly during VYVANSE initiation and after a dosage increase. If serotonin syndrome occurs, discontinue VYVANSE and the CYP2D6 inhibitor [see Warnings and Precautions (5.7) and Overdosage (10)].
Alkalinizing Agents
Clinical Impact | Urinary alkalinizing agents can increase blood levels and potentiate the action of amphetamine.
Intervention | Co-administration of VYVANSE and urinary alkalinizing agents should be avoided.
Acidifying Agents
Clinical Impact | Urinary acidifying agents can lower blood levels and efficacy of amphetamines.
Intervention | Increase dose based on clinical response.
Tricyclic Antidepressants
Clinical Impact | May enhance the activity of tricyclic or sympathomimetic agents causing striking and sustained increases in the concentration of d-amphetamine in the brain; cardiovascular effects can be potentiated.
Intervention | Monitor frequently and adjust or use alternative therapy based on clinical response.

7.2 Drugs Having No Clinically Important Interactions with VYVANSE

From a pharmacokinetic perspective, no dose adjustment of VYVANSE is necessary when VYVANSE is co-administered with guanfacine, venlafaxine, or omeprazole. In addition, no dose adjustment of guanfacine or venlafaxine is needed when VYVANSE is co-administered [see Clinical Pharmacology (12.3)].

From a pharmacokinetic perspective, no dose adjustment for drugs that are substrates of CYP1A2 (e.g., theophylline, duloxetine, melatonin), CYP2D6 (e.g., atomoxetine, desipramine, venlafaxine), CYP2C19 (e.g., omeprazole, lansoprazole, clobazam), and CYP3A4 (e.g., midazolam, pimozide, simvastatin) is necessary when VYVANSE is co-administered [see Clinical Pharmacology (12.3)].

8 USE IN SPECIFIC POPULATIONS

8.1 Pregnancy

Pregnancy Exposure Registry

There is a pregnancy exposure registry that monitors pregnancy outcomes in women exposed to ADHD medications during pregnancy. Healthcare providers are encouraged to register patients by calling the National Pregnancy Registry for Psychostimulants at 1-866-961-2388 or visiting online at https://womensmentalhealth.org/clinical-and researchprograms/pregnancyregistry/adhd-medications/.

Risk Summary

The limited available data from published literature and postmarketing reports on use of VYVANSE in pregnant women are not sufficient to inform a drug-associated risk for major birth defects and miscarriage. Adverse pregnancy outcomes, including premature delivery and low birth weight, have been seen in infants born to mothers dependent on amphetamines [see Clinical Considerations]. In animal reproduction studies, lisdexamfetamine dimesylate (a prodrug of d-amphetamine) had no effects on embryo-fetal morphological development or survival when administered orally to pregnant rats and rabbits throughout the period of organogenesis. Pre- and postnatal studies were not conducted with lisdexamfetamine dimesylate. However, amphetamine (d- to l- ratio of 3:1) administration to pregnant rats during gestation and lactation caused a decrease in pup survival and a decrease in pup body weight that correlated with a delay in developmental landmarks at clinically relevant doses of amphetamine. In addition, adverse effects on reproductive performance were observed in pups whose mothers were treated with amphetamine. Long-term neurochemical and behavioral effects have also been reported in animal developmental studies using clinically relevant doses of amphetamine [see Data].

The estimated background risk of major birth defects and miscarriage for the indicated population is unknown. All pregnancies have a background risk of birth defect, loss or other adverse outcomes. In the U.S. general population, the estimated background risk of major birth defects and miscarriage in clinically recognized pregnancies is 2-4% and 15-20%, respectively.

Clinical Considerations

Fetal/Neonatal Adverse Reactions

Amphetamines, such as VYVANSE, cause vasoconstriction and thereby may decrease placental perfusion. In addition, amphetamines can stimulate uterine contractions increasing the risk of premature delivery. Infants born to amphetamine-dependent mothers have an increased risk of premature delivery and low birth weight.

Monitor infants born to mothers taking amphetamines for symptoms of withdrawal such as feeding difficulties, irritability, agitation, and excessive drowsiness.

Data

Animal Data

Lisdexamfetamine dimesylate had no apparent effects on embryo-fetal morphological development or survival when administered orally to pregnant rats and rabbits throughout the period of organogenesis at doses of up to 40 and 120 mg/kg/day, respectively. These doses are approximately 5.5 and 33 times, respectively, the maximum recommended human dose (MRHD) of 70 mg/day given to adults, on a mg/m^2 body surface area basis.

A study was conducted with amphetamine (d- to l- enantiomer ratio of 3:1) in which pregnant rats received daily oral doses of 2, 6, and 10 mg/kg from gestation day 6 to lactation day 20. All doses caused hyperactivity and decreased weight gain in the dams. A decrease in pup survival was seen at all doses. A decrease in pup body weight was seen at 6 and 10 mg/kg which correlated with delays in developmental landmarks, such as preputial separation and vaginal opening. Increased pup locomotor activity was seen at 10 mg/kg on day 22 postpartum but not at 5 weeks postweaning. When pups were tested for reproductive performance at maturation, gestational weight gain, number of implantations, and number of delivered pups were decreased in the group whose mothers had been given 10 mg/kg.

A number of studies from the literature in rodents indicate that prenatal or early postnatal exposure to amphetamine (d- or d, l-) at doses similar to those used clinically can result in long-term neurochemical and behavioral alterations. Reported behavioral effects include learning and memory deficits, altered locomotor activity, and changes in sexual function.

8.2 Lactation

Risk Summary

Lisdexamfetamine is a pro-drug of dextroamphetamine. Based on limited case reports in published literature, amphetamine (d-or d, l-) is present in human milk, at relative infant doses of 2% to 13.8% of the maternal weight-adjusted dosage and a milk/plasma ratio ranging between 1.9 and 7.5. There are no reports of adverse effects on the breastfed infant. Long-term neurodevelopmental effects on infants from amphetamine exposure are unknown. It is possible that large dosages of dextroamphetamine might interfere with milk production, especially in women whose lactation is not well established. Because of the potential for serious adverse reactions in nursing infants, including serious cardiovascular reactions, blood pressure and heart rate increase, suppression of growth, and peripheral vasculopathy, advise patients that breastfeeding is not recommended during treatment with VYVANSE.

8.4 Pediatric Use

The safety and effectiveness of VYVANSE have not been established in pediatric patients below the age of 6 years.

ADHD

Safety and effectiveness of VYVANSE have been established in pediatric patients with ADHD ages 6 to 17 years [see Dosage and Administration (2.3), Adverse Reactions (6.1), Clinical Pharmacology (12.3), and Clinical Studies (14.1)].

Safety and efficacy of VYVANSE were evaluated in a double-blind, randomized, parallel-group, placebo-controlled, fixed-dose study in pediatric patients ages 4 to 5 years with ADHD, followed by a 1-year open-label extension study. In these studies, patients experienced elevated rates of adverse reactions, including weight loss, decreased BMI, decreased appetite, insomnia, infections (upper respiratory and nasopharyngitis), irritability, and affect lability.

With the same VYVANSE dose, mean steady state exposure of dextroamphetamine was approximately 44% higher in pediatric patients ages 4 to 5 years compared to the pediatric patients ages 6 to 11 years.

BED

Safety and effectiveness of VYVANSE have not been established in pediatric patients with BED less than 18 years of age.

Growth Suppression

Growth should be monitored during treatment with stimulants, including VYVANSE, and pediatric patients who are not growing or gaining weight as expected may need to have their treatment interrupted [see Warnings and Precautions (5.5) and Adverse Reactions (6.1)].

Juvenile Animal Data

Studies conducted in juvenile rats and dogs at clinically relevant doses showed growth suppression that partially or fully reversed in dogs and female rats but not in male rats after a four-week drug-free recovery period.

A study was conducted in which juvenile rats received oral doses of 4, 10, or 40 mg/kg/day of lisdexamfetamine dimesylate from day 7 to day 63 of age. These doses are approximately 0.3, 0.7, and 3 times the maximum recommended human daily dose of 70 mg on a mg/m^2 basis for a child. Dose-related decreases in food consumption, bodyweight gain, and crown-rump length were seen; after a four-week drug-free recovery period, bodyweights and crown-rump lengths had significantly recovered in females but were still substantially reduced in males. Time to vaginal opening was delayed in females at the highest dose, but there were no drug effects on fertility when the animals were mated beginning on day 85 of age.

In a study in which juvenile dogs received lisdexamfetamine dimesylate for 6 months beginning at 10 weeks of age, decreased bodyweight gain was seen at all doses tested (2, 5, and 12 mg/kg/day, which are approximately 0.5, 1, and 3 times the maximum recommended human daily dose on a mg/m^2 basis for a child). This effect partially or fully reversed during a four-week drug-free recovery period.

8.5 Geriatric Use

Clinical studies of VYVANSE did not include sufficient numbers of subjects aged 65 and over to determine whether they respond differently from younger subjects. Other reported clinical experience and pharmacokinetic data [see Clinical Pharmacology (12.3)] have not identified differences in responses between the elderly and younger patients. In general, dose selection for an elderly patient should start at the low end of the dosing range, reflecting the greater frequency of decreased hepatic, renal, or cardiac function, and of concomitant disease or other drug therapy.

8.6 Renal Impairment

Due to reduced clearance in patients with severe renal impairment (GFR 15 to <30 mL/min/1.73 m^2), the maximum dose should not exceed 50 mg/day. The maximum recommended dose in ESRD (GFR <15 mL/min/1.73 m^2) patients is 30 mg/day [see Clinical Pharmacology (12.3)].

Lisdexamfetamine and d-amphetamine are not dialyzable.

9 DRUG ABUSE AND DEPENDENCE

9.1 Controlled Substance

VYVANSE contains lisdexamfetamine, a prodrug of amphetamine, a Schedule II controlled substance.

9.2 Abuse

VYVANSE has a high potential for abuse and misuse which can lead to the development of a substance use disorder, including addiction [see Warnings and Precautions (5.1)]. VYVANSE can be diverted for non-medical use into illicit channels or distribution.

Abuse is the intentional non-therapeutic use of a drug, even once, to achieve a desired psychological or physiological effect. Misuse is the intentional use, for therapeutic purposes, of a drug by an individual in a way other than prescribed by a health care provider or for whom it was not prescribed. Drug addiction is a cluster of behavioral, cognitive, and physiological phenomena that may include a strong desire to take the drug, difficulties in controlling drug use (e.g., continuing drug use despite harmful consequences, giving a higher priority to drug use than other activities and obligations), and possible tolerance or physical dependence.

Misuse and abuse of lisdexamfetamine, a prodrug of amphetamine, may cause increased heart rate, respiratory rate, or blood pressure; sweating; dilated pupils; hyperactivity; restlessness; insomnia; decreased appetite; loss of coordination; tremors; flushed skin; vomiting; and/or abdominal pain. Anxiety, psychosis, hostility, aggression, and suicidal or homicidal ideation have also been observed with CNS stimulants abuse and/or misuse. Misuse and abuse of CNS stimulants, including VYVANSE, can result in overdose and death [see Overdosage (10)], and this risk is increased with higher doses or unapproved methods of administration, such as snorting or injection.

Studies of VYVANSE in Drug Abusers

A randomized, double-blind, placebo-control, cross-over, abuse liability study in 38 patients with a history of drug abuse was conducted with single-doses of 50, 100, or 150 mg of VYVANSE, 40 mg of immediate-release d-amphetamine sulphate (a controlled II substance), and 200 mg of diethylpropion hydrochloride (a controlled IV substance). VYVANSE 100 mg produced significantly less "Drug Liking Effects" as measured by the Drug Rating Questionnaire-Subject score, compared to d-amphetamine 40 mg; and 150 mg of VYVANSE demonstrated similar "Drug-Liking Effects" compared to 40 mg of d-amphetamine and 200 mg of diethylpropion.

Intravenous administration of 50 mg lisdexamfetamine dimesylate to individuals with a history of drug abuse produced positive subjective responses on scales measuring "Drug Liking", "Euphoria", "Amphetamine Effects", and "Benzedrine Effects" that were greater than placebo but less than those produced by an equivalent dose (20 mg) of intravenous d-amphetamine.

9.3 Dependence

Physical Dependence

VYVANSE may produce physical dependence. Physical dependence is a state that develops as a result of physiological adaptation in response to repeated drug use, manifested by withdrawal signs and symptoms after abrupt discontinuation or a significant dose reduction of a drug. Withdrawal signs and symptoms after abrupt discontinuation or dose reduction following prolonged use of CNS stimulants including VYVANSE include dysphoric mood; depression; fatigue; vivid, unpleasant dreams; insomnia or hypersomnia; increased appetite; and psychomotor retardation or agitation.

Tolerance

VYVANSE may produce tolerance. Tolerance is a physiological state characterized by a reduced response to a drug after repeated administration (i.e., a higher dose of a drug is required to produce the same effect that was once obtained at a lower dose).

10 OVERDOSAGE

Clinical Effects of Overdose

Overdose of CNS stimulants is characterized by the following sympathomimetic effects:

- Cardiovascular effects including tachyarrhythmias, and hypertension or hypotension. Vasospasm, myocardial infarction, or aortic dissection may precipitate sudden cardiac death. Takotsubo cardiomyopathy may develop.
- CNS effects including psychomotor agitation, confusion, and hallucinations. Serotonin syndrome, seizures, cerebral vascular accidents, and coma may occur.
- Life-threatening hyperthermia (temperatures greater than 104°F) and rhabdomyolysis may develop.

Overdose Management

Consider the possibility of multiple drug ingestion. The pharmacokinetic profile of VYVANSE should be considered when treating patients with overdose. Lisdexamfetamine and d-amphetamine are not dialyzable. Consider contacting the Poison Help line (1-800-222-1222) or a medical toxicologist for additional overdose management recommendations.

11 DESCRIPTION

VYVANSE (lisdexamfetamine dimesylate), a CNS stimulant, is for once-a-day oral administration. The chemical designation for lisdexamfetamine dimesylate is (2S)-2,6-diamino-N-[(1S)-1-methyl-2-phenylethyl] hexanamide dimethanesulfonate. The molecular formula is C15H25N3O∙(CH4O3S)2, which corresponds to a molecular weight of 455.60. The chemical structure is:

Lisdexamfetamine dimesylate is a white to off-white powder that is soluble in water (792 mg/mL).

Information for VYVANSE capsules:

VYVANSE capsules contain 10 mg, 20 mg, 30 mg, 40 mg, 50 mg, 60 mg, and 70 mg of lisdexamfetamine dimesylate (equivalent to 5.8 mg, 11.6 mg, 17.3 mg, 23.1 mg, 28.9 mg, 34.7 mg, and 40.5 mg of lisdexamfetamine).

Inactive ingredients: microcrystalline cellulose, croscarmellose sodium, and magnesium stearate. The capsule shells contain gelatin, titanium dioxide, and one or more of the following: FD&C Red #3, FD&C Yellow #6, FD&C Blue #1, Black Iron Oxide, and Yellow Iron Oxide.

Information for VYVANSE chewable tablets:

VYVANSE chewable tablets contain 10 mg, 20 mg, 30 mg, 40 mg, 50 mg, and 60 mg of lisdexamfetamine dimesylate (equivalent to 5.8 mg, 11.6 mg, 17.3 mg, 23.1 mg, 28.9 mg, and 34.7 mg of lisdexamfetamine).

Inactive ingredients: colloidal silicon dioxide, croscarmellose sodium, guar gum, magnesium stearate, mannitol, microcrystalline cellulose, sucralose, artificial strawberry flavor.

12 CLINICAL PHARMACOLOGY

12.1 Mechanism of Action

Lisdexamfetamine is a prodrug of dextroamphetamine. Amphetamines are non-catecholamine sympathomimetic amines with CNS stimulant activity. The exact mode of therapeutic action in ADHD and BED is not known.

12.2 Pharmacodynamics

Amphetamines block the reuptake of norepinephrine and dopamine into the presynaptic neuron and increase the release of these monoamines into the extraneuronal space. The parent drug, lisdexamfetamine, does not bind to the sites responsible for the reuptake of norepinephrine and dopamine in vitro.

12.3 Pharmacokinetics

Pharmacokinetic studies after oral administration of lisdexamfetamine dimesylate have been conducted in healthy adult (capsule and chewable tablet formulations) and pediatric (6 to 12 years) patients with ADHD (capsule formulation). After single dose administration of lisdexamfetamine dimesylate, pharmacokinetics of dextroamphetamine was found to be linear between 30 mg and 70 mg in a pediatric study (6 to 12 years), and between 50 mg and 250 mg in an adult study. Dextroamphetamine pharmacokinetic parameters following administration of lisdexamfetamine dimesylate in adults exhibited low inter-subject (<25%) and intra-subject (<8%) variability. There is no accumulation of lisdexamfetamine and dextroamphetamine at steady state in healthy adults.

Absorption

Capsule formulation

Following single-dose oral administration of VYVANSE capsule (30 mg, 50 mg, or 70 mg) in patients ages 6 to 12 years with ADHD under fasted conditions, Tmax of lisdexamfetamine and dextroamphetamine was reached at approximately 1 hour and 3.5 hours post dose, respectively. Weight/Dose normalized AUC and Cmax values were the same in pediatric patients ages 6 to 12 years as the adults following single doses of 30 mg to 70 mg VYVANSE capsule.

Effect of food on capsule formulation

Neither food (a high fat meal or yogurt) nor orange juice affects the observed AUC and Cmax of dextroamphetamine in healthy adults after single-dose oral administration of 70 mg of VYVANSE capsules. Food prolongs Tmax by approximately 1 hour (from 3.8 hours at fasted state to 4.7 hours after a high fat meal or to 4.2 hours with yogurt). After an 8-hour fast, the AUC for dextroamphetamine following oral administration of lisdexamfetamine dimesylate in solution and as intact capsules were equivalent.

Chewable Tablet formulation

After a single dose administration of 60 mg VYVANSE chewable tablet in healthy subjects under fasted conditions, Tmax of lisdexamfetamine and dextroamphetamine was reached at approximately 1 hour and 4.4 hours post dose, respectively. Compared to 60 mg VYVANSE capsule, exposure (Cmax and AUC) to lisdexamfetamine was about 15% lower. The exposure (Cmax and AUCinf) of dextroamphetamine is similar between VYVANSE chewable tablet and VYVANSE capsule.

Effect of food on tablet formulation

Administration of 60 mg VYVANSE chewable tablet with food (a high-fat meal) decreases the exposure (Cmax and AUCinf) of dextroamphetamine by about 5% to 7%, and prolongs mean Tmax by approximately 1 hour (from 3.9 hours at fasted state to 4.9 hours).

Elimination

Plasma concentrations of unconverted lisdexamfetamine are low and transient, generally becoming non-quantifiable by 8 hours after administration. The plasma elimination half-life of lisdexamfetamine typically averaged less than one hour in volunteers ages 6 years and older. The plasma elimination half-life of dextroamphetamine was approximately 8.6 to 9.5 hours in pediatric patients 6 to 12 years and 10 to 11.3 hours in healthy adults.

Metabolism

Lisdexamfetamine is converted to dextroamphetamine and l-lysine primarily in blood due to the hydrolytic activity of red blood cells after oral administration of lisdexamfetamine dimesylate. In vitro data demonstrated that red blood cells have a high capacity for metabolism of lisdexamfetamine; substantial hydrolysis occurred even at low hematocrit levels (33% of normal). Lisdexamfetamine is not metabolized by cytochrome P450 enzymes.

Excretion

Following oral administration of a 70 mg dose of radiolabeled lisdexamfetamine dimesylate to 6 healthy subjects, approximately 96% of the oral dose radioactivity was recovered in the urine and only 0.3% recovered in the feces over a period of 120 hours. Of the radioactivity recovered in the urine, 42% of the dose was related to amphetamine, 25% to hippuric acid, and 2% to intact lisdexamfetamine.

Specific Populations

Exposures of dextroamphetamine in specific populations are summarized in Figure 1.

Figure 1: Specific Populations [Figure 1 shows the geometric mean ratios and the 90% confidence limits for Cmax and AUC of d-amphetamine. Comparison for gender uses males as the reference. Comparison for age uses 55-64 years as the reference.] :

Drug Interaction Studies

Effects of other drugs on the exposures of dextroamphetamine are summarized in Figure 2.

Figure 2: Effect of Other Drugs on VYVANSE:

The effects of VYVANSE on the exposures of other drugs are summarized in Figure 3.

Figure 3: Effect of VYVANSE on Other Drugs:

13 NONCLINICAL TOXICOLOGY

13.1 Carcinogenesis, Mutagenesis, and Impairment of Fertility

Carcinogenesis

Carcinogenicity studies of lisdexamfetamine dimesylate have not been performed. No evidence of carcinogenicity was found in studies in which d-, l-amphetamine (enantiomer ratio of 1:1) was administered to mice and rats in the diet for 2 years at doses of up to 30 mg/kg/day in male mice, 19 mg/kg/day in female mice, and 5 mg/kg/day in male and female rats.

Mutagenesis

Lisdexamfetamine dimesylate was not clastogenic in the mouse bone marrow micronucleus test in vivo and was negative when tested in the E. coli and S. typhimurium components of the Ames test and in the L5178Y/TK+/- mouse lymphoma assay in vitro.

Impairment of Fertility

Amphetamine (d- to l-enantiomer ratio of 3:1) did not adversely affect fertility or early embryonic development in the rat at doses of up to 20 mg/kg/day.

13.2 Animal Toxicology and/or Pharmacology

Acute administration of high doses of amphetamine (d- or d, l-) has been shown to produce long-lasting neurotoxic effects, including irreversible nerve fiber damage, in rodents. The significance of these findings to humans is unknown.

14 CLINICAL STUDIES

14.1 Attention Deficit Hyperactivity Disorder (ADHD)

Pediatric Patients Ages 6 to 12 Years with ADHD

A double-blind, randomized, placebo-controlled, parallel-group study (Study 1) was conducted in pediatric patients ages 6 to 12 years (N=290) who met DSM-IV criteria for ADHD (either the combined type or the hyperactive-impulsive type). Patients were randomized to receive final doses of 30 mg, 50 mg, or 70 mg of VYVANSE or placebo once daily in the morning for a total of four weeks of treatment. All patients receiving VYVANSE were initiated on 30 mg for the first week of treatment. Patients assigned to the 50 mg and 70 mg dose groups were titrated by 20 mg per week until they achieved their assigned dose. The primary efficacy outcome was change in Total Score from baseline to endpoint in investigator ratings on the ADHD Rating Scale (ADHD-RS), an 18-item questionnaire with a score range of 0-54 points that measures the core symptoms of ADHD which includes both hyperactive/impulsive and inattentive subscales. Endpoint was defined as the last post-randomization treatment week (i.e., Weeks 1 through 4) for which a valid score was obtained. All VYVANSE dose groups were superior to placebo in the primary efficacy outcome. Mean effects at all doses were similar; however, the highest dose (70 mg/day) was numerically superior to both lower doses (Study 1 in Table 6). The effects were maintained throughout the day based on parent ratings (Conners' Parent Rating Scale) in the morning (approximately 10 am), afternoon (approximately 2 pm), and early evening (approximately 6 pm).

A double-blind, placebo-controlled, randomized, crossover design, analog classroom study (Study 2) was conducted in pediatric patients ages 6 to 12 years (N=52) who met DSM-IV criteria for ADHD (either the combined type or the hyperactive-impulsive type). Following a 3-week open-label dose optimization with Adderall XR®, patients were randomly assigned to continue their optimized dose of Adderall XR (10 mg, 20 mg, or 30 mg), VYVANSE (30 mg, 50 mg, or 70 mg), or placebo once daily in the morning for 1 week each treatment. Efficacy assessments were conducted at 1, 2, 3, 4.5, 6, 8, 10, and 12 hours post-dose using the Swanson, Kotkin, Agler, M.Flynn, and Pelham Deportment scores (SKAMP-DS), a 4-item subscale of the SKAMP with scores ranging from 0 to 24 points that measures deportment problems leading to classroom disruptions. A significant difference in patient behavior, based upon the average of investigator ratings on the SKAMP-DS across the 8 assessments were observed between patients when they received VYVANSE compared to patients when they received placebo (Study 2 in Table 6). The drug effect reached statistical significance from hours 2 to 12 post-dose, but was not significant at 1 hour.

A second double-blind, placebo-controlled, randomized, crossover design, analog classroom study (Study 3) was conducted in pediatric patients ages 6 to 12 years (N=129) who met DSM-IV criteria for ADHD (either the combined type or the hyperactive-impulsive type). Following a 4-week open-label dose optimization with VYVANSE (30 mg, 50 mg, 70 mg), patients were randomly assigned to continue their optimized dose of VYVANSE or placebo once daily in the morning for 1 week each treatment. A significant difference in patient behavior, based upon the average of investigator ratings on the SKAMP-Deportment scores across all 7 assessments conducted at 1.5, 2.5, 5.0, 7.5, 10.0, 12.0, and 13.0 hours post-dose, were observed between patients when they received VYVANSE compared to patients when they received placebo (Study 3 in Table 6, Figure 4).

Pediatric Patients Ages 13 to 17 Years with ADHD

A double-blind, randomized, placebo-controlled, parallel-group study (Study 4) was conducted in pediatric patients ages 13 to 17 years (N=314) who met DSM-IV criteria for ADHD. In this study, patients were randomized in a 1:1:1:1 ratio to a daily morning dose of VYVANSE (30 mg/day, 50 mg/day or 70 mg/day) or placebo for a total of four weeks of treatment. All patients receiving VYVANSE were initiated on 30 mg for the first week of treatment. Patients assigned to the 50 mg and 70 mg dose groups were titrated by 20 mg per week until they achieved their assigned dose. The primary efficacy outcome was change in Total Score from baseline to endpoint in investigator ratings on the ADHD Rating Scale (ADHD-RS). Endpoint was defined as the last post-randomization treatment week (i.e., Weeks 1 through 4) for which a valid score was obtained. All VYVANSE dose groups were superior to placebo in the primary efficacy outcome (Study 4 in Table 6).

Pediatric Patients Ages 6 to 17 Years: Short-Term Treatment in ADHD

A double-blind, randomized, placebo- and active-controlled parallel-group, dose-optimization study (Study 5) was conducted in pediatric patients ages 6 to 17 years (n=336) who met DSM-IV criteria for ADHD. In this eight-week study, patients were randomized to a daily morning dose of VYVANSE (30, 50 or 70 mg/day), an active control, or placebo (1:1:1). The study consisted of a Screening and Washout Period (up to 42 days), a 7-week Double-blind Evaluation Period (consisting of a 4-week Dose-Optimization Period followed by a 3-week Dose-Maintenance Period), and a 1-week Washout and Follow-up Period. During the Dose Optimization Period, subjects were titrated until an optimal dose, based on tolerability and investigator's judgment, was reached. VYVANSE showed significantly greater efficacy than placebo. The placebo-adjusted mean reduction from baseline in the ADHD-RS-IV total score was 18.6. Subjects on VYVANSE also showed greater improvement on the Clinical Global Impression-Improvement (CGI-I) rating scale compared to subjects on placebo (Study 5 in Table 6).

Pediatric Patients Ages 6 to 17 Years: Maintenance Treatment in ADHD

Maintenance of Efficacy Study (Study 6) – A double-blind, placebo-controlled, randomized withdrawal study was conducted in pediatric patients ages 6 to 17 years (N=276) who met the diagnosis of ADHD (DSM-IV criteria). A total of 276 patients were enrolled into the study, 236 patients participated in Study 5 and 40 subjects directly enrolled. Subjects were treated with open-label VYVANSE for at least 26 weeks prior to being assessed for entry into the randomized withdrawal period. Eligible patients had to demonstrate treatment response as defined by CGI-S <3 and Total Score on the ADHD-RS ≤22. Patients that maintained treatment response for 2 weeks at the end of the open label treatment period were eligible to be randomized to ongoing treatment with the same dose of VYVANSE (N=78) or switched to placebo (N=79) during the double-blind phase. Patients were observed for relapse (treatment failure) during the 6 week double-blind phase. A significantly lower proportion of treatment failures occurred among VYVANSE subjects (15.8%) compared to placebo (67.5%) at endpoint of the randomized withdrawal period. The endpoint measurement was defined as the last post-randomization treatment week at which a valid ADHD-RS Total Score and CGI-S were observed. Treatment failure was defined as a ≥50% increase (worsening) in the ADHD-RS Total Score and a ≥2-point increase in the CGI-S score compared to scores at entry into the double-blind randomized withdrawal phase. Subjects who withdrew from the randomized withdrawal period and who did not provide efficacy data at their last on-treatment visit were classified as treatment failures (Study 6, Figure 5).

Adults: Short-Term Treatment in ADHD

A double-blind, randomized, placebo-controlled, parallel-group study (Study 7) was conducted in adults ages 18 to 55 (N=420) who met DSM-IV criteria for ADHD. In this study, patients were randomized to receive final doses of 30 mg, 50 mg, or 70 mg of VYVANSE or placebo for a total of four weeks of treatment. All patients receiving VYVANSE were initiated on 30 mg for the first week of treatment. Patients assigned to the 50 mg and 70 mg dose groups were titrated by 20 mg per week until they achieved their assigned dose. The primary efficacy outcome was change in Total Score from baseline to endpoint in investigator ratings on the ADHD Rating Scale (ADHD-RS). Endpoint was defined as the last post-randomization treatment week (i.e., Weeks 1 through 4) for which a valid score was obtained. All VYVANSE dose groups were superior to placebo in the primary efficacy outcome (Study 7 in Table 6).

The second study was a multi-center, randomized, double-blind, placebo-controlled, cross-over, modified analog classroom study (Study 8) of VYVANSE to simulate a workplace environment in 142 adults ages 18 to 55 who met DSM-IV-TR criteria for ADHD. There was a 4-week open-label, dose optimization phase with VYVANSE (30 mg/day, 50 mg/day, or 70 mg/day in the morning). Patients were then randomized to one of two treatment sequences: 1) VYVANSE (optimized dose) followed by placebo, each for one week, or 2) placebo followed by VYVANSE, each for one week. Efficacy assessments occurred at the end of each week, using the Permanent Product Measure of Performance (PERMP), a skill-adjusted math test that measures attention in ADHD. PERMP total score results from the sum of the number of math problems attempted plus the number of math problems answered correctly. VYVANSE treatment, compared to placebo, resulted in a statistically significant improvement in attention across all post-dose time points, as measured by average PERMP total scores over the course of one assessment day, as well as at each time point measured. The PERMP assessments were administered at pre-dose (-0.5 hours) and at 2, 4, 8, 10, 12, and 14 hours post-dose (Study 8 in Table 6, Figure 6).

Adults: Maintenance Treatment in ADHD

A double-blind, placebo-controlled, randomized withdrawal design study (Study 9) was conducted in adults ages 18 to 55 (N=123) who had a documented diagnosis of ADHD or met DSM-IV criteria for ADHD. At study entry, patients must have had documentation of treatment with VYVANSE for a minimum of 6 months and had to demonstrate treatment response as defined by Clinical Global Impression Severity (CGI-S) ≤3 and Total Score on the ADHD-RS <22. ADHD-RS Total Score is a measure of core symptoms of ADHD. The CGI-S score assesses the clinician's impression of the patient's current illness state and ranges from 1 (not at all ill) to 7 (extremely ill). Patients that maintained treatment response at Week 3 of the open label treatment phase (N=116) were eligible to be randomized to ongoing treatment with the same dose of VYVANSE (N=56) or switched to placebo (N=60) during the double-blind phase. Patients were observed for relapse (treatment failure) during the 6-week double-blind phase. The efficacy endpoint was the proportion of patients with treatment failure during the double-blind phase. Treatment failure was defined as a ≥50% increase (worsening) in the ADHD-RS Total Score and ≥2-point increase in the CGI-S score compared to scores at entry into the double-blind phase. Maintenance of efficacy for patients treated with VYVANSE was demonstrated by the significantly lower proportion of patients with treatment failure (9%) compared to patients receiving placebo (75%) at endpoint during the double-blind phase (Study 9, Figure 7).

Table 6: Summary of Primary Efficacy Results from Short-term Studies of VYVANSE in Pediatric Patients (Ages 6 to 17) and Adults with ADHD
Study Number (Age range) | Primary Endpoint | Treatment Group | Mean Baseline Score (SD) | LS Mean Change from Baseline (SE) | Placebo-subtracted Difference [Difference (drug minus placebo) in least-squares mean change from baseline.] (95% CI)
Study 1 (6 – 12 years) | ADHD-RS-IV | VYVANSE (30 mg/day) [Doses statistically significantly superior to placebo.] | 43.2 (6.7) | -21.8 (1.6) | -15.6 (-19.9, -11.2)
Study 1 (6 – 12 years) | ADHD-RS-IV | VYVANSE (50 mg/day) | 43.3 (6.7) | -23.4 (1.6) | -17.2 (-21.5, -12.9)
Study 1 (6 – 12 years) | ADHD-RS-IV | VYVANSE (70 mg/day) | 45.1(6.8) | -26.7 (1.5) | -20.5 (-24.8, -16.2)
Study 1 (6 – 12 years) | ADHD-RS-IV | Placebo | 42.4 (7.1) | -6.2 (1.6) | --
Study 2 (6 – 12 years) | Average SKAMP-DS | VYVANSE (30, 50 or 70 mg/day) | -- [Pre-dose SKAMP-DS was not collected.] | 0.8 (0.1) [LS Mean for SKAMP-DS (Study 2 and 3) or PERMP (Study 8) is post-dose average score over all sessions of the treatment day, rather than change from baseline.] | -0.9 (-1.1, -0.7)
Study 2 (6 – 12 years) | Average SKAMP-DS | Placebo | -- | 1.7 (0.1) | --
Study 3 (6 – 12 years) | Average SKAMP-DS | VYVANSE (30, 50 or 70 mg/day) | 0.9 (1.0) [Pre-dose SKAMP-DS (Study 3) or PERMP (Study 8) total score, averaged over both periods.] | 0.7 (0.1) | -0.7 (-0.9, -0.6)
Study 3 (6 – 12 years) | Average SKAMP-DS | Placebo | 0.7 (0.9) | 1.4 (0.1) | --
Study 4 (13 – 17 years) | ADHD-RS-IV | VYVANSE (30 mg/day) | 38.3 (6.7) | -18.3 (1.2) | -5.5 (-9.0, -2.0)
Study 4 (13 – 17 years) | ADHD-RS-IV | VYVANSE (50 mg/day) | 37.3 (6.3) | -21.1 (1.3) | -8.3 (-11.8, -4.8)
Study 4 (13 – 17 years) | ADHD-RS-IV | VYVANSE (70 mg/day) | 37.0 (7.3) | -20.7 (1.3) | -7.9 (-11.4, -4.5)
Study 4 (13 – 17 years) | ADHD-RS-IV | Placebo | 38.5 (7.1) | -12.8 (1.2) | --
Study 5 (6 – 17 years) | ADHD-RS-IV | VYVANSE (30, 50 or 70 mg/day) | 40.7 (7.3) | -24.3 (1.2) | -18.6 (-21.5, -15.7)
Study 5 (6 – 17 years) | ADHD-RS-IV | Placebo | 41.0 (7.1) | -5.7 (1.1) | --
Study 7 (18 – 55 years) | ADHD-RS-IV | VYVANSE (30 mg/day) | 40.5 (6.2) | -16.2 (1.1) | -8.0 (-11.5, -4.6)
Study 7 (18 – 55 years) | ADHD-RS-IV | VYVANSE (50 mg/day) | 40.8 (7.3) | -17.4 (1.0) | -9.2 (-12.6, -5.7)
Study 7 (18 – 55 years) | ADHD-RS-IV | VYVANSE (70 mg/day) | 41.0 (6.0) | -18.6 (1.0) | -10.4 (-13.9, -6.9)
Study 7 (18 – 55 years) | ADHD-RS-IV | Placebo | 39.4 (6.4) | -8.2 (1.4) | --
Study 8 (18 – 55 years) | Average PERMP | VYVANSE (30, 50 or 70 mg/day) | 260.1 (86.2) | 312.9 (8.6) | 23.4 (15.6, 31.2)
Study 8 (18 – 55 years) | Average PERMP | Placebo | 261.4 (75.0) | 289.5 (8.6) | --
SD: standard deviation; SE: standard error; LS Mean: least-squares mean; CI: confidence interval.

Figure 4 LS Mean SKAMP Deportment Subscale Score by Treatment and Time-point for Pediatric Patients Ages 6 to 12 with ADHD after 1 Week of Double-Blind Treatment (Study 3)

Higher score on the SKAMP-Deportment scale indicates more severe symptoms

Figure 5 Kaplan-Meier Estimated Proportion of Patients with Treatment Failure for Pediatric Patients Ages 6 to 17 (Study 6)

Figure 6 LS Mean (SE) PERMP Total Score by Treatment and Time-point for Adults Ages 18 to 55 with ADHD after 1 Week of Double-Blind Treatment (Study 8)

Higher score on the PERMP scale indicates less severe symptoms.

Figure 7 Kaplan-Meier Estimated Proportion of Subjects with Relapse in Adults with ADHD (Study 9)

14.2 Binge Eating Disorder (BED)

A phase 2 study evaluated the efficacy of VYVANSE 30, 50 and 70 mg/day compared to placebo in reducing the number of binge days/week in adults with at least moderate to severe BED. This randomized, double-blind, parallel-group, placebo-controlled, forced-dose titration study (Study 10) consisted of an 11-week double-blind treatment period (3 weeks of forced-dose titration followed by 8 weeks of dose maintenance). VYVANSE 30 mg/day was not statistically different from placebo on the primary endpoint. The 50 and 70 mg/day doses were statistically superior to placebo on the primary endpoint.

The efficacy of VYVANSE in the treatment of BED was demonstrated in two 12-week randomized, double-blind, multi-center, parallel-group, placebo-controlled, dose-optimization studies (Study 11 and Study 12) in adults aged 18-55 years (Study 11: N=374, Study 12: N=350) with moderate to severe BED. A diagnosis of BED was confirmed using DSM-IV criteria for BED. Severity of BED was determined based on having at least 3 binge days per week for 2 weeks prior to the baseline visit and on having a Clinical Global Impression Severity (CGI-S) score of ≥4 at the baseline visit. For both studies, a binge day was defined as a day with at least 1 binge episode, as determined from the subject's daily binge diary.

Both 12-week studies consisted of a 4-week dose-optimization period and an 8-week dose-maintenance period. During dose-optimization, subjects assigned to VYVANSE began treatment at the titration dose of 30 mg/day and, after 1 week of treatment, were subsequently titrated to 50 mg/day. Additional increases to 70 mg/day were made as tolerated and clinically indicated. Following the dose-optimization period, subjects continued on their optimized dose for the duration of the dose-maintenance period.

The primary efficacy outcome for the two studies was defined as the change from baseline at Week 12 in the number of binge days per week. Baseline is defined as the weekly average of the number of binge days per week for the 14 days prior to the baseline visit. Subjects from both studies on VYVANSE had a statistically significantly greater reduction from baseline in mean number of binge days per week at Week 12. In addition, subjects on VYVANSE showed greater improvement as compared to placebo across key secondary outcomes with higher proportion of subjects rated improved on the CGI-I rating scale, higher proportion of subjects with 4-week binge cessation, and greater reduction in the Yale-Brown Obsessive Compulsive Scale Modified for Binge Eating (Y-BOCS-BE) total score.

Table 7: Summary of Primary Efficacy Results in BED
Study Number | Treatment Group | Primary Efficacy Measure: Binge Days per Week at Week 12
 |  | Mean Baseline Score (SD) | LS Mean Change from Baseline (SE) | Placebo-subtracted Difference [Difference (drug minus placebo) in least-squares mean change from baseline.] (95% CI)
Study 11 | VYVANSE (50 or 70 mg/day) [Doses statistically significantly superior to placebo.] | 4.79 (1.27) | -3.87 (0.12) | -1.35 (-1.70, -1.01)
 | Placebo | 4.60 (1.21) | -2.51 (0.13) | --
Study 12 | VYVANSE (50 or 70 mg/day) | 4.66 (1.27) | -3.92 (0.14) | -1.66 (-2.04, -1.28)
 | Placebo | 4.82 (1.42) | -2.26 (0.14) | --
SD: standard deviation; SE: standard error; LS Mean: least-squares mean; CI: confidence interval.

A double-blind, placebo controlled, randomized withdrawal design study (Study 13) was conducted to evaluate maintenance of efficacy based on time to relapse between VYVANSE and placebo in adults aged 18 to 55 (N=267) with moderate to severe BED. In this longer-term study patients who had responded to VYVANSE in the preceding 12-week open-label treatment phase were randomized to continuation of VYVANSE or placebo for up to 26 weeks of observation for relapse. Response in the open-label phase was defined as 1 or fewer binge days each week for four consecutive weeks prior to the last visit at the end of the 12-week open-label phase and a CGI-S score of 2 or less at the same visit. Relapse during the double-blind phase was defined as having 2 or more binge days each week for two consecutive weeks (14 days) prior to any visit and having an increase in CGI-S score of 2 or more points compared to the randomized-withdrawal baseline. Maintenance of efficacy for patients who had an initial response during the open-label period and then continued on VYVANSE during the 26-week double-blind randomized-withdrawal phase was demonstrated with VYVANSE being superior over placebo as measured by time to relapse.

Figure 8 Kaplan-Meier Estimated Proportions of Subjects with Relapse in Adults with BED (Study 13)

Examination of population subgroups based on age (there were no patients over 65), gender, and race did not reveal any clear evidence of differential responsiveness in the treatment of BED.

16 HOW SUPPLIED/STORAGE AND HANDLING

16.1 How Supplied

VYVANSE (lisdexamfetamine dimesylate) capsules:

- VYVANSE capsules 10 mg: pink body/pink cap (imprinted with S489 and 10 mg), bottles of 100, NDC 59417-101-10
- VYVANSE capsules 20 mg: ivory body/ivory cap (imprinted with S489 and 20 mg), bottles of 100, NDC 59417-102-10
- VYVANSE capsules 30 mg: white body/orange cap (imprinted with S489 and 30 mg), bottles of 100, NDC 59417-103-10
- VYVANSE capsules 40 mg: white body/blue green cap (imprinted with S489 and 40 mg), bottles of 100, NDC 59417-104-10
- VYVANSE capsules 50 mg: white body/blue cap (imprinted with S489 and 50 mg), bottles of 100, NDC 59417-105-10
- VYVANSE capsules 60 mg: aqua blue body/aqua blue cap (imprinted with S489 and 60 mg), bottles of 100, NDC 59417-106-10
- VYVANSE capsules 70 mg: blue body/orange cap (imprinted with S489 and 70 mg), bottles of 100, NDC 59417-107-10

VYVANSE (lisdexamfetamine dimesylate) chewable tablets:

- VYVANSE chewable tablets 10 mg: White to off-white round shaped tablet debossed with '10' on one side and 'S489' on the other, bottles of 100, NDC 59417-115-01
- VYVANSE chewable tablets 20 mg: White to off-white hexagonal shaped tablet debossed with '20' on one side and 'S489' on the other, bottles of 100, NDC 59417-116-01
- VYVANSE chewable tablets 30 mg: White to off-white arc triangular shaped tablet debossed with '30' on one side and 'S489' on the other, bottles of 100, NDC 59417-117-01
- VYVANSE chewable tablets 40 mg: White to off-white capsule shaped tablet debossed with '40' on one side and 'S489' on the other, bottles of 100, NDC 59417-118-01
- VYVANSE chewable tablets 50 mg: White to off-white arc square shaped tablet debossed with '50' on one side and 'S489' on the other, bottles of 100, NDC 59417-119-01
- VYVANSE chewable tablets 60 mg: White to off-white arc diamond shaped tablet debossed with '60' on one side and 'S489' on the other, bottles of 100, NDC 59417-120-01

16.2 Storage and Handling

Dispense in a tight, light-resistant container as defined in the USP.

Store at room temperature, 20°C to 25°C (68°F to 77°F). Excursions permitted between 15°C and 30°C (59°F to 86°F) [see USP Controlled Room Temperature].

17 PATIENT COUNSELING INFORMATION

Advise the patient to read the FDA-approved patient labeling (Medication Guide).

Abuse, Misuse, and Addiction

Educate patients and their families about the risks of abuse, misuse, and addiction of VYVANSE, which can lead to overdose and death, and proper disposal of any unused drug [see Warnings and Precautions (5.1), Drug Abuse and Dependence (9.2), Overdosage (10)]. Advise patients to store VYVANSE in a safe place, preferably locked, and instruct patients to not give VYVANSE to anyone else.

Risks to Patients with Serious Cardiac Disease

Advise patients that there are potential risks to patients with serious cardiac disease, including sudden death, with VYVANSE use. Instruct patients to contact a healthcare provider immediately if they develop symptoms such as exertional chest pain, unexplained syncope, or other symptoms suggestive of cardiac disease [see Warnings and Precautions (5.2)].

Increased Blood Pressure and Heart Rate

Instruct patients that VYVANSE can cause elevations of their blood pressure and pulse rate and they should be monitored for such effects.

Psychiatric Adverse Reactions

Advise patients that VYVANSE at recommended doses may cause psychotic or manic symptoms even in patients without prior history of psychotic symptoms or mania [see Warnings and Precautions (5.4)].

Long-Term Suppression of Growth in Pediatric Patients

Advise patients that VYVANSE may cause slowing of growth including weight loss [see Warnings and Precautions (5.5)].

Circulation problems in fingers and toes [Peripheral vasculopathy, including Raynaud's phenomenon]

Instruct patients beginning treatment with VYVANSE about the risk of peripheral vasculopathy, including Raynaud's phenomenon, and associated signs and symptoms: fingers or toes may feel numb, cool, painful, and/or may change from pale, to blue, to red. Instruct patients to report to their physician any new numbness, pain, skin color change, or sensitivity to temperature in fingers or toes. Instruct patients to call their physician immediately with any signs of unexplained wounds appearing on fingers or toes while taking VYVANSE. Further clinical evaluation (e.g., rheumatology referral) may be appropriate for certain patients [see Warnings and Precautions (5.6)].

Serotonin Syndrome

Caution patients about the risk of serotonin syndrome with concomitant use of VYVANSE and other serotonergic drugs including SSRIs, SNRIs, triptans, tricyclic antidepressants, fentanyl, lithium, tramadol, tryptophan, buspirone, St. John's Wort, and with drugs that impair metabolism of serotonin (in particular MAOIs, both those intended to treat psychiatric disorders and also others such as linezolid [see Contraindications (4), Warnings and Precautions (5.7) and Drug Interactions (7.1)]. Advise patients to contact their healthcare provider or report to the emergency room if they experience signs or symptoms of serotonin syndrome.

Concomitant Medications

Advise patients to notify their physicians if they are taking, or plan to take, any prescription or over-the-counter drugs because there is a potential for interactions [see Drug Interactions (7.1)].

Motor and Verbal Tics, and Worsening of Tourette's Syndrome

Advise patients that motor and verbal tics and worsening of Tourette's Syndrome may occur during treatment with VYVANSE. Instruct patients to notify their healthcare provider if emergence of new tics or worsening of tics or Tourette's syndrome occurs [see Warnings and Precautions (5.8)].

Pregnancy Registry

Advise patients that there is a pregnancy exposure registry that monitors pregnancy outcomes in women exposed to VYVANSE during pregnancy [see Use in Specific Populations (8.1)].

Pregnancy

Advise patients of the potential fetal effects from the use of VYVANSE during pregnancy. Advise patients to notify their healthcare provider if they become pregnant or intend to become pregnant during treatment with VYVANSE [see Use in Specific Populations (8.1)].

Lactation

Advise women not to breastfeed if they are taking VYVANSE [see Use in Specific Populations (8.2)].

Administration Instructions

- Capsules: Advise patients to take the capsules whole or empty and mix the entire contents with yogurt, water, or orange juice. Advise patients to consume the mixture immediately and not to store for future use [see Dosage and Administration (2.2)].
- Chewable tablets: Advise patients that chewable tablets must be chewed thoroughly before swallowing [see Dosage and Administration (2.2)].

Distributed by:
Takeda Pharmaceuticals America, Inc.
Cambridge, MA 02142

Made in USA

For more information call 1-800-828-2088

VYVANSE, the VYVANSE Logo, and ADDERALL XR are registered trademarks of Takeda Pharmaceuticals U.S.A., Inc.

©2025 Takeda Pharmaceuticals U.S.A., Inc. All rights reserved.

MEDICATION GUIDE
VYVANSE® (Vi' – vans)
(lisdexamfetamine dimesylate)
Capsules and Chewable Tablets, CII

What is the most important information I should know about VYVANSE?
VYVANSE may cause serious side effects, including:

  - Abuse, misuse, and addiction. VYVANSE has a high chance for abuse and misuse and may lead to substance use problems, including addiction. Misuse and abuse of VYVANSE, other amphetamine containing medicines, and methylphenidate containing medicines, can lead to overdose and death. The risk of overdose and death is increased with higher doses of VYVANSE or when it is used in ways that are not approved, such as snorting or injection.
  - Your healthcare provider should check you or your child's risk for abuse, misuse, and addiction before starting treatment with VYVANSE and will monitor you or your child during treatment.
  - VYVANSE may lead to physical dependence after prolonged use, even if taken as directed by your healthcare provider.
  - Do not give VYVANSE to anyone else. See "What is VYVANSE?" for more information.
  - Keep VYVANSE in a safe place and properly dispose of any unused medicine. See "How should I store VYVANSE?" for more information.
  - Tell your healthcare provider if you or your child have ever abused or been dependent on alcohol, prescription medicines, or street drugs.

- Risks for people with serious heart disease. Sudden death has happened in people who have heart defects or other serious heart disease.
  Your healthcare provider should check you or your child carefully for heart problems before starting treatment with VYVANSE. Tell your healthcare provider if you or your child have any heart problems, heart disease, or heart defects.
  Call your healthcare provider right away or go to the nearest hospital emergency room right away if you or your child have any signs of heart problems such as chest pain, shortness of breath, or fainting during treatment with VYVANSE.
- Increased blood pressure and heart rate.
  Your healthcare provider should check you or your child's blood pressure and heart rate regularly during treatment with VYVANSE.
- Mental (psychiatric) problems, including:
  - new or worse behavior and thought problems
  - new or worse bipolar illness
  - new psychotic symptoms (such as hearing voices, or seeing or believing things that are not real) or new manic symptoms
  Tell your healthcare provider about any mental problems you or your child have or about a family history of suicide, bipolar illness, or depression.
  Call your healthcare provider right away if you or your child have any new or worsening mental symptoms or problems during treatment with VYVANSE, especially hearing voices, seeing or believing things that are not real, or new manic symptoms.

What is VYVANSE?
VYVANSE is a central nervous system (CNS) stimulant prescription medicine used for the treatment of:

- Attention Deficit Hyperactivity Disorder (ADHD) in adults and children 6 years of age and older. VYVANSE may help increase attention and decrease impulsiveness and hyperactivity in people with ADHD.
- Moderate to severe binge eating disorder (BED) in adults. VYVANSE may help reduce the number of binge eating days in people with BED.

VYVANSE is not recommended for use in children under 6 years of age with ADHD.
VYVANSE is not for weight loss. It is not known if VYVANSE is safe and effective for the treatment of obesity.
It is not known if VYVANSE is safe and effective for use in children with BED.
VYVANSE is a federally controlled substance (CII) because it contains lisdexamfetamine dimesylate that can be a target for people who abuse prescription medicines or street drugs. Keep VYVANSE in a safe place to protect it from theft. Never give your VYVANSE to anyone else because it may cause death or harm them. Selling or giving away VYVANSE may harm others and is against the law.

Do not take VYVANSE if you or your child are:

- allergic to amphetamine products or any of the ingredients in VYVANSE. See the end of this Medication Guide for a complete list of ingredients in VYVANSE.
- taking, or have stopped taking in the last 14 days, a medicine called a Monoamine Oxidase Inhibitor (MAOI).
- being treated with the antibiotic linezolid or intravenous methylene blue.

Before taking VYVANSE, tell your healthcare provider about all medical conditions, including if you or your child:

- have heart problems, heart disease, heart defects, or high blood pressure
- have mental problems including psychosis, mania, bipolar illness, or depression or have a family history of suicide, bipolar illness, or depression
- have circulation problems in fingers and toes
- have kidney problems
- have or had repeated movements or sounds (tics) or Tourette's syndrome, or have a family history of tics or Tourette's syndrome
- are pregnant or plan to become pregnant. VYVANSE may harm the unborn baby.
  - There is a pregnancy registry for females who are exposed to VYVANSE during pregnancy. The purpose of the registry is to collect information about the health of females exposed to VYVANSE and their baby. If you or your child becomes pregnant during treatment with VYVANSE, talk to your healthcare provider about registering with the National Pregnancy Registry for Psychostimulants at 1-866-961-2388 or visit online at https://womensmentalhealth.org/clinical-and-research-programs/pregnancyregistry/adhd-medications/.
- are breastfeeding or plan to breastfeed. VYVANSE passes into breast milk. You should not breastfeed during treatment with VYVANSE. Talk to your healthcare provider about the best way to feed the baby during treatment with VYVANSE.

Tell your healthcare provider about all the medicines that you or your child take, including prescription and over-the-counter medicines, vitamins, and herbal supplements.
VYVANSE can affect the way other medicines work and other medicines may affect how VYVANSE works. Taking VYVANSE with other medicines can cause serious side effects. Sometimes the doses of other medicines will need to be changed while taking VYVANSE.
Especially tell your healthcare provider if you or your child take:

- selective serotonin reuptake inhibitors (SSRIs)
- medicines used to treat migraine headaches called triptans
- lithium
- tramadol
- buspirone

- serotonin norepinephrine reuptake inhibitors (SNRIs)
- tricyclic antidepressants
- fentanyl
- tryptophan
- St. John's Wort

Keep a list of all medicines to show your healthcare provider and pharmacist when you get a new medicine. Your healthcare provider will decide if VYVANSE can be taken with other medicines.
Do not start any new medicine during treatment with VYVANSE without talking to your healthcare provider first.

How should VYVANSE be taken?

- Take VYVANSE exactly as prescribed by your healthcare provider.
- Your healthcare provider may change the dose if needed.
- Take VYVANSE 1 time each day in the morning with or without food.
- VYVANSE comes in capsules or chewable tablets.
  Taking VYVANSE Capsules:
  - VYVANSE capsules may be swallowed whole.
  - If VYVANSE capsules cannot be swallowed whole, the capsule may be opened and the entire contents sprinkled onto yogurt, or poured into water or orange juice.
    - Using a spoon, break apart any powder that is stuck together. Stir the VYVANSE powder and yogurt, water, or orange juice until they are completely mixed together.
    - Swallow all the yogurt, water, or orange juice mixture right away. Do not store the yogurt, water, or orange juice mixture.
    - It is normal to see a filmy coating on the inside of your glass or container after you eat or drink all the VYVANSE mixture.
  Taking VYVANSE Chewable Tablets:
  - Chew VYVANSE tablets completely before swallowing.

If you or your child take too much VYVANSE, call your healthcare provider or Poison Help line at 1-800-222-1222 or go to the nearest hospital emergency room right away.

What are the possible side effects of VYVANSE?
VYVANSE may cause serious side effects, including:

- See "What is the most important information I should know about VYVANSE?"
- Slowing of growth (height and weight) in children. Children should have their height and weight checked often during treatment with VYVANSE. VYVANSE treatment may be stopped if your child is not growing or gaining weight.
- Circulation problems in fingers and toes (Peripheral vasculopathy, including Raynaud's phenomenon). Signs and symptoms may include:
  - Fingers or toes may feel numb, cool, painful
  - Fingers or toes may change color from pale, to blue, to red
  Tell your healthcare provider if you or your child have numbness, pain, skin color change, or sensitivity to temperature in your fingers or toes.
  Call your healthcare provider right away if you or your child have any signs of unexplained wounds appearing on fingers or toes during treatment with VYVANSE.
- New or worsening tics or worsening Tourette's syndrome. Tell your healthcare provider if you or your child get any new or worsening tics or worsening Tourette's syndrome during treatment with VYVANSE.
- Serotonin Syndrome. A potentially life-threatening problem called serotonin syndrome may happen when VYVANSE is taken with certain other medicines. Stop taking VYVANSE and call your healthcare provider or go to the nearest hospital emergency room right away if you or your child develop any of the following signs and symptoms of serotonin syndrome:

- agitation
- flushing
- coma
- loss of coordination
- dizziness
- seeing or hearing things that are not real (hallucination)
- high body temperature (hyperthermia)

- fast heartbeat
- seizures
- sweating
- confusion
- tremors, stiff muscles, or muscle twitching
- changes in blood pressure
- nausea, vomiting, diarrhea

The most common side effects of VYVANSE in children 6 to 17 years old and adults with ADHD include:

- loss of appetite (anorexia)
- decreased appetite
- diarrhea
- dry mouth
- trouble sleeping
- stomach pain

- anxiety
- weight loss
- dizziness
- irritability
- nausea
- vomiting

The most common side effects of VYVANSE in adults with BED include:

- dry mouth
- decreased appetite
- constipation
- anxiety

- trouble sleeping
- increased heart rate
- feeling jittery

These are not all the possible side effects of VYVANSE.
Call your doctor for medical advice about side effects. You may report side effects to FDA at 1-800-FDA-1088.

How should I store VYVANSE?

- Store VYVANSE in a safe place (like a locked cabinet) and in a tightly closed container at room temperature between 68°F to 77°F (20°C to 25°C).
- Protect VYVANSE from light.
- Dispose of remaining, unused, or expired VYVANSE by a medicine take-back program at a U.S. Drug Enforcement Administration (DEA) authorized collection site. If no take-back program or DEA authorized collector is available, mix VYVANSE with an undesirable, nontoxic substance such as dirt, cat litter, or used coffee grounds to make it less appealing to children and pets. Place the mixture in a container such as a sealed plastic bag and throw away VYVANSE in the household trash. Visit www.fda.gov/drugdisposal for additional information on disposal of unused medicines.

Keep VYVANSE and all medicines out of the reach of children.

General information about the safe and effective use of VYVANSE.
Medicines are sometimes prescribed for purposes other than those listed in a Medication Guide. Do not use VYVANSE for a condition for which it was not prescribed. Do not give VYVANSE to other people, even if they have the same symptoms that you have. It may harm them and it is against the law. You can ask your pharmacist or healthcare provider for information about VYVANSE that is written for healthcare professionals.

What are the ingredients in VYVANSE?
Active ingredient: lisdexamfetamine dimesylate
Capsule Inactive ingredients: microcrystalline cellulose, croscarmellose sodium, and magnesium stearate. The capsule shells (imprinted with S489) contain gelatin, titanium dioxide, and one or more of the following: FD&C Red #3, FD&C Yellow #6, FD&C Blue #1, Black Iron Oxide, and Yellow Iron Oxide.
Chewable Tablet Inactive ingredients: colloidal silicon dioxide, croscarmellose sodium, guar gum, magnesium stearate, mannitol, microcrystalline cellulose, sucralose, artificial strawberry flavor.
Distributed by: Takeda Pharmaceuticals America, Inc., Cambridge, MA 02142. VYVANSE and the VYVANSE Logo are registered trademarks of Takeda Pharmaceuticals U.S.A., Inc. © 2025 Takeda Pharmaceuticals U.S.A., Inc. All rights reserved.
For more information, go to www.vyvanse.com or call 1-800-828-2088.

This Medication Guide has been approved by the U.S. Food and Drug Administration.

Revised: 09/2025

PRINCIPAL DISPLAY PANEL - 10 mg Capsule Bottle Label

NDC 59417-101-10

Vyvanse®
(lisdexamfetamine
dimesylate) capsules

10 mg

CII
Rx only

100 CAPSULES

Takeda

PRINCIPAL DISPLAY PANEL - 20 mg Capsule Bottle Label

NDC 59417-102-10

Vyvanse®
(lisdexamfetamine
dimesylate) capsules

20 mg

CII
Rx only

100 CAPSULES

Takeda

PRINCIPAL DISPLAY PANEL - 30 mg Capsule Bottle Label

NDC 59417-103-10

Vyvanse®
(lisdexamfetamine
dimesylate) capsules

30 mg

CII
Rx only

100 CAPSULES

Takeda

PRINCIPAL DISPLAY PANEL - 40 mg Capsule Bottle Label

NDC 59417-104-10

Vyvanse®
(lisdexamfetamine
dimesylate) capsules

40 mg

CII
Rx only

100 CAPSULES

Takeda

PRINCIPAL DISPLAY PANEL - 50 mg Capsule Bottle Label

NDC 59417-105-10

Vyvanse®
(lisdexamfetamine
dimesylate) capsules

50 mg

CII
Rx only

100 CAPSULES

Takeda

PRINCIPAL DISPLAY PANEL - 60 mg Capsule Bottle Label

NDC 59417-106-10

Vyvanse®
(lisdexamfetamine
dimesylate) capsules

60 mg

CII
Rx only

100 CAPSULES

Takeda

PRINCIPAL DISPLAY PANEL - 70 mg Capsule Bottle Label

NDC 59417-107-10

Vyvanse®
(lisdexamfetamine
dimesylate) capsules

70 mg

CII
Rx only

100 CAPSULES

Takeda

PRINCIPAL DISPLAY PANEL - 10 mg Tablet Bottle Label

NDC 59417-115-01

Vyvanse®
(lisdexamfetamine
dimesylate) chewable tablets

10 mg

100 CHEWABLE
TABLETS

Chew tablets completely
before swallowing. Do
not swallow tablets whole.

CII
Rx only

Takeda

PRINCIPAL DISPLAY PANEL - 20 mg Tablet Bottle Label

NDC 59417-116-01

Vyvanse®
(lisdexamfetamine
dimesylate) chewable tablets

20 mg

100 CHEWABLE
TABLETS

Chew tablets completely
before swallowing. Do
not swallow tablets whole.

CII
Rx only

Takeda

PRINCIPAL DISPLAY PANEL - 30 mg Tablet Bottle Label

NDC 59417-117-01

Vyvanse®
(lisdexamfetamine
dimesylate) chewable tablets

30 mg

100 CHEWABLE
TABLETS

Chew tablets completely
before swallowing. Do
not swallow tablets whole.

CII
Rx only

Takeda

PRINCIPAL DISPLAY PANEL - 40 mg Tablet Bottle Label

NDC 59417-118-01

Vyvanse®
(lisdexamfetamine
dimesylate) chewable tablets

40 mg

100 CHEWABLE
TABLETS

Chew tablets completely
before swallowing. Do
not swallow tablets whole.

CII
Rx only

Takeda

PRINCIPAL DISPLAY PANEL - 50 mg Tablet Bottle Label

NDC 59417-119-01

Vyvanse®
(lisdexamfetamine
dimesylate) chewable tablets

50 mg

100 CHEWABLE
TABLETS

Chew tablets completely
before swallowing. Do
not swallow tablets whole.

CII
Rx only

Takeda

PRINCIPAL DISPLAY PANEL - 60 mg Tablet Bottle Label

NDC 59417-120-01

Vyvanse®
(lisdexamfetamine
dimesylate) chewable tablets

60 mg

100 CHEWABLE
TABLETS

Chew tablets completely
before swallowing. Do
not swallow tablets whole.

CII
Rx only

Takeda